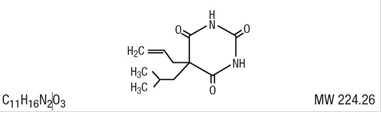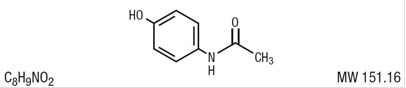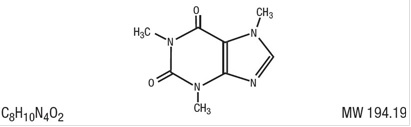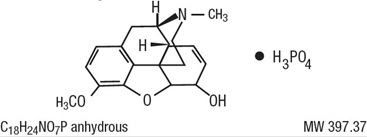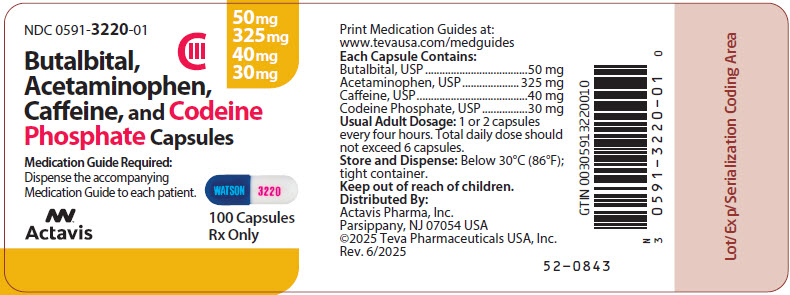 DRUG LABEL: Butalbital, Acetaminophen, Caffeine, and Codeine Phosphate
NDC: 0591-3220 | Form: CAPSULE
Manufacturer: Actavis Pharma, Inc.
Category: prescription | Type: HUMAN PRESCRIPTION DRUG LABEL
Date: 20260109
DEA Schedule: CIII

ACTIVE INGREDIENTS: CODEINE PHOSPHATE 30 mg/1 1; BUTALBITAL 50 mg/1 1; CAFFEINE 40 mg/1 1; ACETAMINOPHEN 325 mg/1 1
INACTIVE INGREDIENTS: SILICON DIOXIDE; MAGNESIUM STEARATE; STARCH, CORN; D&C RED NO. 33; FD&C BLUE NO. 1; GELATIN; TITANIUM DIOXIDE; D&C RED NO. 7

HIGHLIGHTS OF PRESCRIBING INFORMATION

These highlights do not include all the information needed to use Butalbital, Acetaminophen, Caffeine, and Codeine Phosphate Capsules safely and effectively. See full prescribing information for Butalbital, Acetaminophen, Caffeine, and Codeine Phosphate Capsules.
Butalbital, Acetaminophen, Caffeine, and Codeine Phosphate Capsules for oral use, CIII
Initial U.S. Approval: 1992

RECENT MAJOR CHANGES

Boxed Warning 12/2025

Indications and Usage (1) 12/2025

Dosage and Administration (2.2, 2.5) 12/2025

Warnings and Precautions (5.1, 5.2, 5.3, 5.15, 5.18) 12/2025

WARNING: SERIOUS AND LIFE-THREATENING RISKS FROM USE OF BUTALBITAL, ACETAMINOPHEN, CAFFEINE, AND CODEINE PHOSPHATE CAPSULES

See full prescribing information for complete boxed warning.

- Butalbital, Acetaminophen, Caffeine, and Codeine Phosphate Capsules expose users to the risks of addiction, abuse, and misuse, which can lead to overdose and death. Assess patient's risk before prescribing and reassess regularly for these behaviors and conditions. (5.1)
- Serious, life-threatening, or fatal respiratory depression may occur, especially during initiation and following a dosage increase. To reduce the risk of respiratory depression, proper dosing and titration of Butalbital, Acetaminophen, Caffeine, and Codeine Phosphate Capsules are essential. (5.2)
- Accidental ingestion of Butalbital, Acetaminophen, Caffeine, and Codeine Phosphate Capsules, especially by children, can result in fatal overdose. Keep out of reach of children. (5.2)
- Concomitant use of opioids or a barbiturate with benzodiazepines or other central nervous system (CNS) depressants, including alcohol, may result in profound sedation, respiratory depression, coma, and death. Reserve concomitant prescribing for use in patients for whom alternative treatment options are inadequate. (5.3, 7)
- Advise pregnant women using opioids for an extended period of time of the risk of Neonatal Opioid Withdrawal Syndrome, which may be life-threatening if not recognized and treated. Ensure that management by neonatology experts will be available at delivery. (5.4)
- Healthcare providers are strongly encouraged to complete a REMS-compliant education program and to counsel patients and caregivers on serious risks, safe use, and the importance of reading the Medication Guide with each prescription. (5.5)
- Life-threatening respiratory depression and death have occurred in children who received codeine; most cases followed tonsillectomy and/or adenoidectomy, and many of the children had evidence of being an ultra-rapid metabolizer of codeine due to a CYP2D6 polymorphism. (5.6). Butalbital, Acetaminophen, Caffeine, and Codeine Phosphate Capsules are contraindicated in children younger than 12 years of age and in children younger than 18 years of age following tonsillectomy and/or adenoidectomy (4). Avoid the use of Butalbital, Acetaminophen, Caffeine, and Codeine Phosphate Capsules in adolescents 12 to 18 years of age who have other risk factors that may increase their sensitivity to the respiratory depressant effects of codeine.
- The effects of concomitant use or discontinuation of cytochrome P450 3A4 inducers, 3A4 inhibitors, or 2D6 inhibitors with codeine are complex. Use of cytochrome P450 3A4 inducers, 3A4 inhibitors, or 2D6 inhibitors with Butalbital, Acetaminophen, Caffeine, and Codeine Phosphate Capsules requires careful consideration of the effects on codeine, and the active metabolite, morphine. (5.7, 7)
- Acetaminophen has been associated with cases of acute liver failure, at times resulting in liver transplant and death. Most of the cases of liver injury are associated with the use of acetaminophen at doses that exceed 4,000 milligrams per day, and often involve more than one acetaminophen-containing product. (5.8)

1 INDICATIONS AND USAGE

Butalbital, Acetaminophen, Caffeine, and Codeine Phosphate Capsule is a combination product of butalbital, a barbiturate; acetaminophen; caffeine, a methylxanthine; and codeine phosphate, an opioid agonist; and is indicated for the management of the symptom complex of tension (or muscle contraction) headache, when other non-opioid analgesic and alternative treatments are inadequate. (1)

Limitations of Use

- Because of the risks of addiction, abuse, misuse, overdose, and death, which can occur at any dosage or duration, and persist over the course of therapy, reserve opioid analgesics, including Butalbital, Acetaminophen, Caffeine, and Codeine Phosphate Capsules, for use in patients for whom alternative treatment options are ineffective, not tolerated, or would be otherwise inadequate to provide sufficient management of pain. (1, 5.1)

2 DOSAGE AND ADMINISTRATION

- Butalbital, Acetaminophen, Caffeine, and Codeine Phosphate Capsules should be prescribed only by healthcare professionals who are knowledgeable about the use of opioids and how to mitigate the associated risks. (2.1)
- Use the lowest effective dosage for the shortest duration of time consistent with individual patient treatment goals. Reserve titration to higher doses of Butalbital, Acetaminophen, Caffeine, and Codeine Phosphate Capsules for patients in whom lower doses are insufficiently effective and in whom the expected benefits of using a higher dose opioid clearly outweigh the substantial risks. (2.1, 5)
- Many acute pain conditions (e.g., the pain that occurs with a number of surgical procedures or acute musculoskeletal injuries) require no more than a few days of an opioid analgesic. Clinical guidelines on opioid prescribing for some acute pain conditions are available. (2.1)
- Initiate the dosing regimen for each patient individually, taking into account the patient’s underlying cause and severity of pain, prior analgesic treatment and response, and risk factors for addiction, abuse, and misuse. (2.1, 5.1)
- Respiratory depression can occur at any time during opioid therapy, especially when initiating and following dosage increases with Butalbital, Acetaminophen, Caffeine, and Codeine Phosphate Capsules. Consider this risk when selecting an initial dose and when making dose adjustments. (2.1, 5.2)
- Discuss opioid overdose reversal agents and options for acquiring them with the patient and/or caregiver, both when initiating and renewing treatment with Butalbital, Acetaminophen, Caffeine, and Codeine Phosphate capsules, especially if the patient has additional risk factors for overdose, or close contacts at risk for exposure and overdose. (2.2, 5.1, 5.2, 5.3)
- Initiate treatment with one or two capsules every 4 hours as needed for pain and at the lowest dose necessary to achieve adequate analgesia. Titrate the dose based upon the individual patient’s response to their initial dose of Butalbital, Acetaminophen, Caffeine, and Codeine Phosphate Capsules. Total daily dosage should not exceed 6 capsules. (2.3, 5)
- Periodically reassess patients receiving Butalbital, Acetaminophen, Caffeine, and Codeine Phosphate Capsules to evaluate the continued need for opioid analgesics to maintain pain control, for the signs or symptoms of adverse reactions, and for the development of addiction, abuse, or misuse. (2.4)
- Do not rapidly reduce or abruptly discontinue Butalbital, Acetaminophen, Caffeine, and Codeine Phosphate Capsules in a physically dependent patient because rapid reduction or abrupt discontinuation of opioid analgesics has resulted in serious withdrawal symptoms, uncontrolled pain, and suicide. (2.5, 5.18)

3 DOSAGE FORMS AND STRENGTHS

- Capsules: 50 mg butalbital, 325 mg acetaminophen, 40 mg caffeine, and 30 mg codeine phosphate. (3)

4 CONTRAINDICATIONS

- Children younger than 12 years of age. (4)
- Post-operative management in children younger than 18 years of age following tonsillectomy and/or adenoidectomy. (4)
- Significant respiratory depression. (4)
- Acute or severe bronchial asthma in an unmonitored setting or in absence of resuscitative equipment. (4)
- Concurrent use of monoamine oxidase inhibitors (MAOIs) or use of MAOIs within the last 14 days. (4)
- Known or suspected gastrointestinal obstruction, including paralytic ileus. (4)
- Intolerance or hypersensitivity to acetaminophen, caffeine, butalbital or codeine, or components of Butalbital, Acetaminophen, Caffeine, and Codeine Phosphate Capsules. (4)
- Porphyria. (4)

5 WARNINGS AND PRECAUTIONS

- Opioid-Induced Hyperalgesia and Allodynia: Opioid-Induced Hyperalgesia (OIH) occurs when an opioid analgesic paradoxically causes an increase in pain, or an increase in sensitivity to pain. If OIH is suspected, carefully consider appropriately decreasing the dose of the current opioid analgesic or opioid rotation. (5.9)
- Life-Threatening Respiratory Depression in Patients with Chronic Pulmonary Disease or in Elderly, Cachectic, or Debilitated Patients: Regularly evaluate patients, particularly during initiation and titration. (5.10)
- Adrenal Insufficiency: If diagnosed, treat with physiologic replacement of corticosteroids, and wean patient off of the opioid. (5.12)
- Severe Hypotension: Regularly evaluate patients during dosage initiation and titration. Avoid use of Butalbital, Acetaminophen, Caffeine, and Codeine Phosphate Capsules in patients with circulatory shock. (5.13)
- Risks of Use in Patients with Increased Intracranial Pressure, Brain Tumors, Head Injury, or Impaired Consciousness: Monitor for sedation and respiratory depression. Avoid use of Butalbital, Acetaminophen, Caffeine, and Codeine Phosphate Capsules in patients with impaired consciousness or coma. (5.14)

6 ADVERSE REACTIONS

Frequently reported adverse reactions are drowsiness, lightheadedness, dizziness, sedation, shortness of breath, nausea, vomiting, abdominal pain, and intoxicated feeling. (6)

To report SUSPECTED ADVERSE REACTIONS, contact Actavis Pharma LLC at 1-800-272-5525 or FDA at 1-800-FDA-1088 or www.fda.gov/medwatch.

7 DRUG INTERACTIONS

- Serotonergic Drugs: Concomitant use may result in serotonin syndrome. Discontinue Butalbital, Acetaminophen, Caffeine, and Codeine Phosphate Capsules if serotonin syndrome is suspected. (7)
- Mixed Agonist/Antagonist and Partial Agonist Opioid Analgesics: Avoid use with Butalbital, Acetaminophen, Caffeine, and Codeine Phosphate Capsules because they may reduce analgesic effect of Butalbital, Acetaminophen, Caffeine, and Codeine Phosphate Capsules or precipitate withdrawal symptoms. (7)

8 USE IN SPECIFIC POPULATIONS

- Pregnancy: May cause fetal harm. (8.1)
- Lactation: Breastfeeding not recommended. (8.2)
- Geriatric: Respiratory depression has occurred after large initial doses were administered. Increase dosage slowly. (8.5)

FULL PRESCRIBING INFORMATION

WARNING: SERIOUS AND LIFE-THREATENING RISKS FROM USE OF BUTALBITAL, ACETAMINOPHEN, CAFFEINE, AND CODEINE PHOSPHATE CAPSULES

Addiction, Abuse, and Misuse

Because the use of Butalbital, Acetaminophen, Caffeine, and Codeine Phosphate Capsules exposes patients and other users to the risks of opioid addiction, abuse, and misuse, which can lead to overdose and death, assess each patient’s risk prior to prescribing and reassess all patients regularly for the development of these behaviors and conditions [see Warnings and Precautions (5.1)].

Life-Threatening Respiratory Depression

Serious, life-threatening, or fatal respiratory depression may occur with use of Butalbital, Acetaminophen, Caffeine, and Codeine Phosphate Capsules, especially during initiation or following a dosage increase. To reduce the risk of respiratory depression, proper dosing and titration of Butalbital, Acetaminophen, Caffeine, and Codeine Phosphate Capsules are essential [see Warnings and Precautions (5.2)].

Accidental Ingestion

Accidental ingestion of even one dose of Butalbital, Acetaminophen, Caffeine, and Codeine Phosphate Capsules, especially by children, can result in a fatal overdose of codeine [see Warnings and Precautions (5.2)].

Risks From Concomitant Use With Benzodiazepines Or Other CNS Depressants

Concomitant use of opioids with benzodiazepines or other central nervous system (CNS) depressants, including alcohol, may result in profound sedation, respiratory depression, coma, and death. Reserve concomitant prescribing of Butalbital, Acetaminophen, Caffeine, and Codeine Phosphate Capsules and benzodiazepines or other CNS depressants for use in patients for whom alternative treatment options are inadequate [see Warnings and Precautions (5.3), Drug Interactions (7)].

Neonatal Opioid Withdrawal Syndrome (NOWS)

Advise pregnant women using opioids for an extended period of time of the risk of Neonatal Opioid Withdrawal Syndrome, which may be life-threatening if not recognized and treated. Ensure that management by neonatology experts will be available at delivery [see Warnings and Precautions (5.4)].

Opioid Analgesic Risk Evaluation and Mitigation Strategy (REMS)

Healthcare providers are strongly encouraged to complete a REMS-compliant education program and to counsel patients and caregivers on serious risks, safe use, and the importance of reading the Medication Guide with each prescription [see Warnings and Precautions (5.5)].

Ultra-Rapid Metabolism of Codeine and Other Risk Factors for Life-threatening Respiratory Depression in Children

Life-threatening respiratory depression and death have occurred in children who received codeine. Most of the reported cases occurred following tonsillectomy and/or adenoidectomy, and many of the children had evidence of being an ultra-rapid metabolizer of codeine due to a CYP2D6 polymorphism [see Warnings and Precautions (5.6)]. Butalbital, Acetaminophen, Caffeine, and Codeine Phosphate Capsules are contraindicated in children younger than 12 years of age and in children younger than 18 years of age following tonsillectomy and/or adenoidectomy [see Contraindications (4)]. Avoid the use of Butalbital, Acetaminophen, Caffeine, and Codeine Phosphate Capsules in adolescents 12 to 18 years of age who have other risk factors that may increase their sensitivity to the respiratory depressant effects of codeine.

Interactions with Drugs Affecting Cytochrome P450 Isoenzymes

The effects of concomitant use or discontinuation of cytochrome P450 3A4 inducers, 3A4 inhibitors, or 2D6 inhibitors with codeine are complex. Use of cytochrome P450 3A4 inducers, 3A4 inhibitors, or 2D6 inhibitors with Butalbital, Acetaminophen, Caffeine, and Codeine Phosphate Capsules requires careful consideration of the effects on codeine, and the active metabolite, morphine [see Warnings and Precautions (5.7)].

Hepatotoxicity

Butalbital, Acetaminophen, Caffeine, and Codeine Phosphate Capsules contain acetaminophen. Acetaminophen has been associated with cases of acute liver failure, at times resulting in liver transplant and death. Most of the cases of liver injury are associated with the use of acetaminophen at doses that exceed 4,000 milligrams per day, and often involve more than one acetaminophen-containing product [see Warnings and Precautions (5.8)].

1 INDICATIONS AND USAGE

Butalbital, Acetaminophen, Caffeine, and Codeine Phosphate Capsules are indicated for the management of the symptom complex of tension (or muscle contraction) headache when non-opioid analgesic and alternative treatments are inadequate.

Limitations of Use

- Because of the risks of addiction, abuse, misuse, overdose, and death, which can occur at any dosage or duration, and persist over the course of therapy, [see Warnings and Precautions (5.1)], reserve opioid analgesics, including Butalbital, Acetaminophen, Caffeine, and Codeine Phosphate Capsules, for use in patients for whom alternative treatment options are ineffective, not tolerated, or would be otherwise inadequate to provide sufficient management of pain.

2 DOSAGE AND ADMINISTRATION

2.1 Important Dosage and Administration Instructions

- Butalbital, Acetaminophen, Caffeine, and Codeine Phosphate Capsules should be prescribed only by healthcare professionals who are knowledgeable about the use of opioids and how to mitigate the associated risks.
- Use the lowest effective dosage for the shortest duration of time consistent with individual patient treatment goals [see Warnings and Precautions (5)]. Because the risk of overdose increases as opioid doses increase, reserve titration to higher doses of Butalbital, Acetaminophen, Caffeine, and Codeine Phosphate Capsules for patients in whom lower doses are insufficiently effective and in whom the expected benefits of using a higher dose opioid clearly outweigh the substantial risks.
- Many acute pain conditions (e.g., the pain that occurs with a number of surgical procedures or acute musculoskeletal injuries) require no more than a few days of an opioid analgesic. Clinical guidelines on opioid prescribing for some acute pain conditions are available.
- There is variability in the opioid analgesic dose and duration needed to adequately manage pain due both to the cause of pain and to individual patient factors. Initiate the dosing regimen for each patient individually, taking into account the patient’s underlying cause and severity of pain, prior analgesic treatment and response, and risk factors for addiction, abuse, and misuse [see Warnings and Precautions (5.1)].
- Respiratory depression can occur at any time during opioid therapy, especially when initiating and following dosage increases with Butalbital, Acetaminophen, Caffeine, and Codeine Phosphate Capsules. Consider this risk when selecting an initial dose and when making dose adjustments [see Warnings and Precautions (5.2)].

Evidence supporting the efficacy and safety of Butalbital, Acetaminophen, Caffeine, and Codeine Phosphate Capsules in the treatment of multiple recurrent headaches is unavailable.

2.2 Patient Access to an Opioid Overdose Reversal Agent for the Emergency Treatment of Opioid Overdose

Inform patients and caregivers about opioid overdose reversal agents (e.g., naloxone, nalmefene). Discuss the importance of having access to an opioid overdose reversal agent, especially if the patient has risk factors for overdose (e.g., concomitant use of CNS depressants, a history of opioid use disorder, or prior opioid overdose) or if there are household members (including children) or other close contacts at risk for accidental ingestion or opioid overdose. The presence of risk factors for overdose should not prevent the management of pain in any patient [see Warnings and Precautions (5.1, 5.2, 5.3)].

Discuss the options for obtaining an opioid overdose reversal agent (e.g., prescription, over-the-counter, or as part of a community-based program) [see Warnings and Precautions (5.2)].

There are important differences among the opioid overdose reversal agents, such as route of administration, product strength, approved patient age range, and pharmacokinetics. Be familiar with these differences, as outlined in the approved labeling for those products, prior to recommending or prescribing such an agent.

2.3 Dosing Information

One or two capsules every 4 hours as needed for pain. Total daily dosage should not exceed 6 capsules. Use the lowest dose necessary to achieve adequate analgesia. Titrate the dose based upon the individual patient’s response to their initial dose of Butalbital, Acetaminophen, Caffeine, and Codeine Phosphate Capsules.

2.4 Titration and Maintenance of Therapy

Individually titrate Butalbital, Acetaminophen, Caffeine, and Codeine Phosphate Capsules to a dose that provides adequate analgesia and minimizes adverse reactions. Continually reevaluate patients receiving Butalbital, Acetaminophen, Caffeine, and Codeine Phosphate Capsules to assess the maintenance of pain control, signs and symptoms of opioid withdrawal, and other adverse reactions, as well as to reassess for the development of addiction, abuse, or misuse [see Warnings and Precautions (5.1, 5.18)]. Frequent communication is important among the prescriber, other members of the healthcare team, the patient, and the caregiver/family during periods of changing analgesic requirements, including initial titration.

If the level of pain increases after dosage stabilization, attempt to identify the source of increased pain before increasing the Butalbital, Acetaminophen, Caffeine, and Codeine Phosphate Capsules dosage. If after increasing the dosage, unacceptable opioid-related adverse reactions are observed (including an increase in pain after a dosage increase), consider reducing the dosage [see Warnings and Precautions (5)]. Adjust the dosage to obtain an appropriate balance between management of pain and opioid-related adverse reactions.

2.5 Safe Reduction or Discontinuation of Butalbital, Acetaminophen, Caffeine, and Codeine Phosphate Capsules

Do not rapidly reduce or abruptly discontinue Butalbital, Acetaminophen, Caffeine, and Codeine Phosphate Capsules in patients who may be physically dependent on opioids. Rapid reduction or abrupt discontinuation of opioid analgesics in patients who are physically dependent on opioids has resulted in serious withdrawal symptoms, uncontrolled pain, and suicide. Rapid reduction or abrupt discontinuation has also been associated with attempts to find other sources of opioid analgesics, which may be confused with drug-seeking for abuse. Patients may also attempt to treat their pain or withdrawal symptoms with illicit opioids, such as heroin, and other substances.

When a decision has been made to decrease the dose or discontinue therapy in an opioid-dependent patient taking Butalbital, Acetaminophen, Caffeine, and Codeine Phosphate Capsules, there are a variety of factors that should be considered, including the total daily dose of opioid (including Butalbital, Acetaminophen, Caffeine, and Codeine Phosphate Capsules) the patient has been taking, the duration of treatment, the type of pain being treated, and the physical and psychological attributes of the patient. It is important to ensure ongoing care of the patient and to agree on an appropriate tapering schedule and follow-up plan so that patient and provider goals and expectations are clear and realistic. When opioid analgesics are being discontinued due to a suspected substance use disorder, evaluate and treat the patient, or refer for evaluation and treatment of the substance use disorder. Treatment should include evidence-based approaches, such as medication-assisted treatment of opioid use disorder. Complex patients with co-morbid pain and substance use disorders may benefit from referral to a specialist.

There are no standard opioid tapering schedules that are suitable for all patients. Good clinical practice dictates a patient-specific plan to taper the dose of the opioid gradually. For patients on Butalbital, Acetaminophen, Caffeine, and Codeine Phosphate Capsules who are physically opioid-dependent, initiate the taper by a small enough increment (e.g., no greater than 10% to 25% of the total daily dose) to avoid withdrawal symptoms, and proceed with dose-lowering at an interval of every 2 to 4 weeks. Patients who have been taking opioids for briefer periods of time may tolerate a more rapid taper.

It may be necessary to provide the patient with lower dosage strengths to accomplish a successful taper. Reassess the patient frequently to manage pain and withdrawal symptoms, should they emerge. Common withdrawal symptoms include restlessness, lacrimation, rhinorrhea, yawning, perspiration, chills, myalgia, and mydriasis. Other signs and symptoms also may develop, including irritability, anxiety, backache, joint pain, weakness, abdominal cramps, insomnia, nausea, anorexia, vomiting, diarrhea, or increased blood pressure, respiratory rate, or heart rate. If withdrawal symptoms arise, it may be necessary to pause the taper for a period of time or raise the dose of the opioid analgesic to the previous dose, and then proceed with a slower taper. In addition, evaluate patients for any changes in mood, emergence of suicidal thoughts, or use of other substances.

When managing patients taking opioid analgesics, particularly those who have been treated for an extended period of time and/or with high doses for chronic pain, ensure that a multimodal approach to pain management, including mental health support (if needed), is in place prior to initiating an opioid analgesic taper. A multimodal approach to pain management may optimize the treatment of chronic pain, as well as assist with the successful tapering of the opioid analgesic [see Warnings and Precautions (5.18), Drug Abuse and Dependence (9.3)].

3 DOSAGE FORMS AND STRENGTHS

Capsules: Butalbital 50 mg, Acetaminophen 325 mg, Caffeine 40 mg, Codeine Phosphate 30 mg

Dark blue, opaque cap is imprinted with “WATSON” in light blue. White, opaque body is imprinted with “3220” in red.

4 CONTRAINDICATIONS

Butalbital, Acetaminophen, Caffeine, and Codeine Phosphate Capsules are contraindicated for:

- All children younger than 12 years of age [see Warnings and Precautions (5.6)]
- Post-operative management in children younger than 18 years of age following tonsillectomy and/or adenoidectomy [see Warnings and Precautions (5.6)]

Butalbital, Acetaminophen, Caffeine, and Codeine Phosphate Capsules are also contraindicated in patients with:

- Significant respiratory depression [see Warnings and Precautions (5.2)]
- Acute or severe bronchial asthma in an unmonitored setting or in the absence of resuscitative equipment [see Warnings and Precautions (5.10)]
- Concurrent use of monoamine oxidase inhibitors (MAOIs) or use of MAOIs within the last 14 days [see Warnings and Precautions (5.11), Drug Interactions (7)]
- Known or suspected gastrointestinal obstruction, including paralytic ileus [see Warnings and Precautions (5.15)]
- Known intolerance or hypersensitivity to acetaminophen, caffeine, butalbital, or codeine or to the components of Butalbital, Acetaminophen, Caffeine, and Codeine Phosphate Capsules
- Porphyria

5 WARNINGS AND PRECAUTIONS

5.1 Addiction, Abuse, and Misuse

Butalbital, Acetaminophen, Caffeine, and Codeine Phosphate Capsules contain codeine. Codeine in combination with butalbital, acetaminophen, and caffeine is a Schedule III controlled substance. As Butalbital, Acetaminophen, Caffeine, and Codeine Phosphate Capsules contain butalbital and codeine, they expose users to the risks of addiction, abuse, and misuse [see Drug Abuse and Dependence (9)].

Although the risk of addiction in any individual is unknown, it can occur in patients appropriately prescribed Butalbital, Acetaminophen, Caffeine, and Codeine Phosphate Capsules. Addiction can occur at recommended dosages and if the drug is misused or abused. The risk of opioid-related overdose or overdose-related death is increased with higher opioid doses, and this risk persists over the course of therapy. In postmarketing studies, addiction, abuse, misuse, and fatal and non-fatal opioid overdose were observed in patients with long-term opioid use [see Adverse Reactions (6)].

Assess each patient’s risk for addiction, abuse, or misuse prior to prescribing Butalbital, Acetaminophen, Caffeine, and Codeine Phosphate Capsules, and reassess all patients receiving Butalbital, Acetaminophen, Caffeine, and Codeine Phosphate Capsules for the development of these behaviors and conditions. Risks are increased in patients with a personal or family history of substance abuse (including drug or alcohol abuse or addiction) or mental illness (e.g., major depression). The potential for these risks should not, however, prevent the proper management of pain in any given patient. Patients at increased risk may be prescribed opioids such as Butalbital, Acetaminophen, Caffeine, and Codeine Phosphate Capsules but use in such patients necessitates intensive counseling about the risks and proper use of Butalbital, Acetaminophen, Caffeine, and Codeine Phosphate Capsules along with frequent reevaluation for signs of addiction, abuse, and misuse.

Consider recommending or prescribing an opioid overdose reversal agent [see Dosage and Administration (2.2), Warnings and Precautions (5.2)].

Opioids and barbiturates are sought for nonmedical use and are subject to diversion from legitimate prescribed use. Consider these risks when prescribing or dispensing Butalbital, Acetaminophen, Caffeine, and Codeine Phosphate Capsules. Strategies to reduce these risks include prescribing the drug in the smallest appropriate quantity and advising the patient on careful storage of the drug during the course of treatment and on the proper disposal of unused drug. Contact local state professional licensing board or state-controlled substances authority for information on how to prevent and detect abuse or diversion of this product.

5.2 Life-Threatening Respiratory Depression

Serious, life-threatening, or fatal respiratory depression has been reported with the use of opioids, even when used as recommended. Respiratory depression, if not immediately recognized and treated, may lead to respiratory arrest and death. Management of respiratory depression may include close observation, supportive measures, and use of opioid overdose reversal agents, depending on the patient’s clinical status [see Overdosage (10)].

Carbon dioxide (CO2) retention from opioid-induced respiratory depression can exacerbate the sedating effects of opioids.

While serious, life-threatening, or fatal respiratory depression can occur at any time during the use of Butalbital, Acetaminophen, Caffeine, and Codeine Phosphate Capsules, the risk is greatest during the initiation of therapy or following a dosage increase.

To reduce the risk of respiratory depression, proper dosing and titration of Butalbital, Acetaminophen, Caffeine, and Codeine Phosphate Capsules are essential [see Dosage and Administration (2.3)]. Overestimating the Butalbital, Acetaminophen, Caffeine, and Codeine Phosphate Capsules dosage when converting patients from another opioid product can result in a fatal overdose with the first dose.

Accidental ingestion of even one dose of Butalbital, Acetaminophen, Caffeine, and Codeine Phosphate Capsules, especially by children, can result in respiratory depression and death due to an overdose of codeine and butalbital.

Educate patients and caregivers on how to recognize respiratory depression and emphasize the importance of calling 911 or getting emergency medical help right away in the event of a known or suspected overdose.

Opioids can cause sleep-related breathing disorders including central sleep apnea (CSA) and sleep-related hypoxemia. Opioid use increases the risk of CSA in a dose-dependent fashion. In patients who present with CSA, consider decreasing the opioid dosage using best practices for opioid taper [see Dosage and Administration (2.5)].

Patient Access to an Opioid Overdose Reversal Agent for the Emergency Treatment of Opioid Overdose

Inform patients and caregivers about opioid overdose reversal agents (e.g., naloxone, nalmefene). Discuss the importance of having access to an opioid overdose reversal agent, especially if the patient has risk factors for overdose (e.g., concomitant use of CNS depressants, a history of opioid use disorder, or prior opioid overdose) or if there are household members (including children) or other close contacts at risk for accidental ingestion or opioid overdose. The presence of risk factors for overdose should not prevent the management of pain in any patient [see Warnings and Precautions (5.1, 5.3).

Discuss the options for obtaining an opioid overdose reversal agent (e.g., prescription, over-the-counter, or as part of a community-based program).

There are important differences among the opioid overdose reversal agents, such as route of administration, product strength, approved patient age range, and pharmacokinetics. Be familiar with these differences, as outlined in the approved labeling for those products, prior to recommending or prescribing such an agent.

Educate patients and caregivers on how to recognize respiratory depression, and how to use an opioid overdose reversal agent for the emergency treatment of opioid overdose. Emphasize the importance of calling 911 or getting emergency medical help, even if an opioid overdose reversal agent is administered [see Dosage and Administration (2.2), Warnings and Precautions (5.1, 5.3), Overdosage (10)].

5.3 Risks from Concomitant Use with Benzodiazepines or Other CNS Depressants

Profound sedation, respiratory depression, coma, and death may result from the concomitant use of Butalbital, Acetaminophen, Caffeine, and Codeine Phosphate Capsules with benzodiazepines and/or other CNS depressants, including alcohol (e.g., non-benzodiazepine sedatives/hypnotics, anxiolytics, tranquilizers, muscle relaxants, general anesthetics, antipsychotics, gabapentinoids [gabapentin or pregabalin], and other opioids). Because of these risks, reserve concomitant prescribing of these drugs for use in patients for whom alternative treatment options are inadequate.

Observational studies have demonstrated that concomitant use of opioid analgesics and benzodiazepines increases the risk of drug-related mortality compared to use of opioid analgesics alone. Because of similar pharmacological properties, it is reasonable to expect similar risk with the concomitant use of other CNS depressant drugs with opioid analgesics [see Drug Interactions (7)].

If the decision is made to prescribe a benzodiazepine or other CNS depressant concomitantly with an opioid analgesic, prescribe the lowest effective dosages and minimum durations of concomitant use. In patients already receiving an opioid analgesic, prescribe a lower initial dose of the benzodiazepine or other CNS depressant than indicated in the absence of an opioid, and titrate based on clinical response. If an opioid analgesic is initiated in a patient already taking a benzodiazepine or other CNS depressant, prescribe a lower initial dose of the opioid analgesic, and titrate based on clinical response. Inform patients and caregivers of this potential interaction and educate them on the signs and symptoms of respiratory depression (including sedation).

If concomitant use is warranted, consider recommending or prescribing an opioid overdose reversal agent [see Dosage and Administration (2.2), Warnings and Precautions (5.2), Overdosage (10)].

Advise both patients and caregivers about the risks of respiratory depression and sedation when Butalbital, Acetaminophen, Caffeine, and Codeine Phosphate Capsules are used with benzodiazepines or other CNS depressants (including alcohol and illicit drugs). Advise patients not to drive or operate heavy machinery until the effects of concomitant use of the benzodiazepine or other CNS depressant have been determined. Screen patients for risk of substance use disorders, including opioid abuse and misuse, and warn them of the risk for overdose and death associated with the use of additional CNS depressants including alcohol and illicit drugs [see Drug Interactions (7).

5.4 Neonatal Opioid Withdrawal Syndrome

Use of Butalbital, Acetaminophen, Caffeine, and Codeine Phosphate Capsules for an extended period of time during pregnancy can result in withdrawal in the neonate. Neonatal opioid withdrawal syndrome, unlike opioid withdrawal syndrome in adults, may be life-threatening if not recognized and treated, and requires management according to protocols developed by neonatology experts. Observe newborns for signs of neonatal opioid withdrawal syndrome and manage accordingly. Advise pregnant women using opioids for an extended period of time of the risk of neonatal opioid withdrawal syndrome and ensure that appropriate treatment will be available [see Use in Specific Populations (8.1).

5.5 Opioid Analgesic Risk Evaluation and Mitigation Strategy (REMS)

To ensure that the benefits of opioid analgesics outweigh the risks of addiction, abuse, and misuse, the Food and Drug Administration (FDA) has required a Risk Evaluation and Mitigation Strategy (REMS) for these products. Under the requirements of the REMS, drug companies with approved opioid analgesic products must make REMS-compliant education programs available to healthcare providers. Healthcare providers are strongly encouraged to do all of the following:

- Complete a REMS-compliant education program offered by an accredited provider of continuing education (CE) or another education program that includes all the elements of the FDA Education Blueprint for Health Care Providers Involved in the Management or Support of Patients with Pain.
- Discuss the safe use, serious risks, and proper storage and disposal of opioid analgesics with patients and/or their caregivers every time these medicines are prescribed. The Patient Counseling Guide (PCG) can be obtained at this link: www.fda.gov/OpioidAnalgesicREMSPCG.
- Emphasize to patients and their caregivers the importance of reading the Medication Guide that they will receive from their pharmacist every time an opioid analgesic is dispensed to them.
- Consider using other tools to improve patient, household, and community safety, such as patient-prescriber agreements that reinforce patient-prescriber responsibilities.

To obtain further information on the opioid analgesic REMS and for a list of accredited REMS CME/CE, call 1-800-503-0784, or log on to www.opioidanalgesicrems.com. The FDA Blueprint can be found at www.fda.gov/OpioidAnalgesicREMSBlueprint.

5.6 Ultra-Rapid Metabolism of Codeine and Other Risk Factors for Life-threatening Respiratory Depression in Children

Life-threatening respiratory depression and death have occurred in children who received codeine. Codeine is subject to variability in metabolism based upon CYP2D6 genotype (described below), which can lead to an increased exposure to the active metabolite morphine. Based upon post-marketing reports, children younger than 12 years of age appear to be more susceptible to the respiratory depressant effects of codeine, particularly if there are risk factors for respiratory depression. For example, many reported cases of death occurred in the post-operative period following tonsillectomy and/or adenoidectomy, and many of the children had evidence of being ultra-rapid metabolizers of codeine. Furthermore, children with obstructive sleep apnea who are treated with codeine for post-tonsillectomy and/or adenoidectomy pain may be particularly sensitive to its respiratory depressant effect.

Because of the risk of life-threatening respiratory depression and death:

- Butalbital, Acetaminophen, Caffeine, and Codeine Phosphate Capsules are contraindicated for all children younger than 12 years of age [see Contraindications (4)].
- Butalbital, Acetaminophen, Caffeine, and Codeine Phosphate Capsules are contraindicated for post-operative management in pediatric patients younger than 18 years of age following tonsillectomy and/or adenoidectomy [see Contraindications (4)].
- Avoid the use of Butalbital, Acetaminophen, Caffeine, and Codeine Phosphate Capsules in adolescents 12 to 18 years of age who have other risk factors that may increase their sensitivity to the respiratory depressant effects of codeine unless the benefits outweigh the risks. Risk factors include conditions associated with hypoventilation, such as post-operative status, obstructive sleep apnea, obesity, severe pulmonary disease, neuromuscular disease, and concomitant use of other medications that cause respiratory depression.
- As with adults, when prescribing codeine for adolescents, healthcare providers should choose the lowest effective dose for the shortest period of time and inform patients and caregivers about these risks and the signs of morphine overdose [see Use in Specific Populations (8), Overdosage (10)].

Nursing Mothers

At least one death was reported in a nursing infant who was exposed to high levels of morphine in breast milk because the mother was an ultra-rapid metabolizer of codeine. Breastfeeding is not recommended during treatment with Butalbital, Acetaminophen, Caffeine, and Codeine Phosphate Capsules [see Use in Specific Populations (8.2)].

CYP2D6 Genetic Variability: Ultra-rapid metabolizer

Some individuals may be ultra-rapid metabolizers because of a specific CYP2D6 genotype (gene duplications denoted as *1/*1xN or *1/*2xN). The prevalence of this CYP2D6 phenotype varies widely and has been estimated at 1 to 10% for Whites (European, North American), 3 to 4% for Blacks (African Americans), 1 to 2% for East Asians (Chinese, Japanese, Korean), and may be greater than 10% in certain racial/ethnic groups (i.e., Oceanian, Northern African, Middle Eastern, Ashkenazi Jews, Puerto Rican).

These individuals convert codeine into its active metabolite, morphine, more rapidly and completely than other people. This rapid conversion results in higher than expected serum morphine levels. Even at labeled dosage regimens, individuals who are ultra-rapid metabolizers may have life-threatening or fatal respiratory depression or experience signs of overdose (such as extreme sleepiness, confusion, or shallow breathing) [see Overdosage (10)]. Therefore, individuals who are ultra-rapid metabolizers should not use Butalbital, Acetaminophen, Caffeine, and Codeine Phosphate Capsules.

5.7 Risks of Interactions with Drugs Affecting Cytochrome P450 Isoenzymes

The effects of concomitant use or discontinuation of cytochrome P450 3A4 inducers, 3A4 inhibitors, or 2D6 inhibitors with codeine are complex. Use of cytochrome P450 3A4 inducers, 3A4 inhibitors, or 2D6 inhibitors with Butalbital, Acetaminophen, Caffeine, and Codeine Phosphate Capsules require careful consideration of the effects on codeine and the active metabolite, morphine.

- Cytochrome P450 3A4 Interaction
  The concomitant use of Butalbital, Acetaminophen, Caffeine, and Codeine Phosphate Capsules with all cytochrome P450 3A4 inhibitors, such as macrolide antibiotics (e.g., erythromycin), azole-antifungal agents (e.g., ketoconazole), and protease inhibitors (e.g., ritonavir) or discontinuation of a cytochrome P450 3A4 inducer such as rifampin, carbamazepine, and phenytoin, may result in an increase in codeine plasma concentrations with subsequently greater metabolism by cytochrome P450 2D6, resulting in greater morphine levels, which could increase or prolong adverse reactions and may cause potentially fatal respiratory depression.
  The concomitant use of Butalbital, Acetaminophen, Caffeine, and Codeine Phosphate Capsules with all cytochrome P450 3A4 inducers or discontinuation of a cytochrome P450 3A4 inhibitor may result in lower codeine levels, greater norcodeine levels, and less metabolism via 2D6 with resultant lower morphine levels. This may be associated with a decrease in efficacy, and in some patients, may result in signs and symptoms of opioid withdrawal.
  Evaluate patients receiving Butalbital, Acetaminophen, Caffeine, and Codeine Phosphate Capsules and any CYP3A4 inhibitor or inducer at frequent intervals for signs and symptoms that may reflect opioid toxicity and opioid withdrawal when Butalbital, Acetaminophen, Caffeine, and Codeine Phosphate Capsules are used in conjunction with inhibitors and inducers of CYP3A4.
  If concomitant use of a CYP3A4 inhibitor is necessary or if a CYP3A4 inducer is discontinued, consider dosage reduction of Butalbital, Acetaminophen, Caffeine, and Codeine Phosphate Capsules until stable drug effects are achieved. Evaluate patients at frequent intervals for respiratory depression and sedation.
  If concomitant use of a CYP3A4 inducer is necessary or if a CYP3A4 inhibitor is discontinued, consider increasing the Butalbital, Acetaminophen, Caffeine, and Codeine Phosphate Capsules dosage until stable drug effects are achieved. Evaluate patients at frequent intervals for signs of opioid withdrawal [see Drug Interactions (7)].
- Risks of Concomitant Use or Discontinuation of Cytochrome P450 2D6 Inhibitors
  The concomitant use of Butalbital, Acetaminophen, Caffeine, and Codeine Phosphate Capsules with all cytochrome P450 2D6 inhibitors (e.g., amiodarone, quinidine) may result in an increase in codeine plasma concentrations and a decrease in active metabolite morphine plasma concentration which could result in an analgesic efficacy reduction or symptoms of opioid withdrawal.
  Discontinuation of a concomitantly used cytochrome P450 2D6 inhibitor may result in a decrease in codeine plasma concentration and an increase in active metabolite morphine plasma concentration which could increase or prolong adverse reactions and may cause potentially fatal respiratory depression.
  Evaluate patients receiving Butalbital, Acetaminophen, Caffeine, and Codeine Phosphate Capsules and any CYP2D6 inhibitor at frequent intervals for signs and symptoms that may reflect opioid toxicity and opioid withdrawal when Butalbital, Acetaminophen, Caffeine, and Codeine Phosphate Capsules are used in conjunction with inhibitors of CYP2D6.
  If concomitant use with a CYP2D6 inhibitor is necessary, evaluate patients at frequent intervals for signs of reduced efficacy or opioid withdrawal and consider increasing the Butalbital, Acetaminophen, Caffeine, and Codeine Phosphate Capsules dosage. After stopping use of a CYP2D6 inhibitor, consider reducing the Butalbital, Acetaminophen, Caffeine, and Codeine Phosphate Capsules dosage and evaluate patients at frequent intervals for signs and symptoms of respiratory depression or sedation [see Drug Interactions (7)].

5.8 Hepatotoxicity

Butalbital, Acetaminophen, Caffeine, and Codeine Phosphate Capsules contain acetaminophen. Acetaminophen has been associated with cases of acute liver failure, at times resulting in liver transplant and death. Most of the cases of liver injury are associated with the use of acetaminophen at doses that exceed 4000 milligrams per day, and often involve more than one acetaminophen-containing product. The excessive intake of acetaminophen may be intentional to cause self-harm or unintentional as patients attempt to obtain more pain relief or unknowingly take other acetaminophen-containing products.

The risk of acute liver failure is higher in individuals with underlying liver disease and in individuals who ingest alcohol while taking acetaminophen.

Instruct patients to look for acetaminophen or APAP on package labels and not to use more than one product that contains acetaminophen. Instruct patients to seek medical attention immediately upon ingestion of more than 4000 milligrams of acetaminophen per day, even if they feel well.

5.9 Opioid-Induced Hyperalgesia and Allodynia

Opioid-Induced Hyperalgesia (OIH) occurs when an opioid analgesic paradoxically causes an increase in pain, or an increase in sensitivity to pain. This condition differs from tolerance, which is the need for increasing doses of opioids to maintain a defined effect [see Dependence (9.3)].

Symptoms of OIH include (but may not be limited to) increased levels of pain upon opioid dosage increase, decreased levels of pain upon opioid dosage decrease, or pain from ordinarily non-painful stimuli (allodynia). These symptoms may suggest OIH only if there is no evidence of underlying disease progression, opioid tolerance, opioid withdrawal, or addictive behavior.

Cases of OIH have been reported, both with short-term and longer-term use of opioid analgesics. Though the mechanism of OIH is not fully understood, multiple biochemical pathways have been implicated. Medical literature suggests a strong biologic plausibility between opioid analgesics and OIH and allodynia. If a patient is suspected to be experiencing OIH, carefully consider appropriately decreasing the dose of the current opioid analgesic or opioid rotation (safely switching the patient to a different opioid moiety) [see Dosage and Administration (2.5), Warnings and Precautions (5.18)].

5.10 Life-Threatening Respiratory Depression in Patients with Chronic Pulmonary Disease or in Elderly, Cachectic, or Debilitated Patients

The use of Butalbital, Acetaminophen, Caffeine, and Codeine Phosphate Capsules in patients with acute or severe bronchial asthma in an unmonitored setting or in the absence of resuscitative equipment is contraindicated.

Patients with Chronic Pulmonary Disease: Butalbital, Acetaminophen, Caffeine, and Codeine Phosphate Capsules-treated patients with significant chronic obstructive pulmonary disease or cor pulmonale, and those with a substantially decreased respiratory reserve, hypoxia, hypercapnia, or pre-existing respiratory depression are at increased risk of decreased respiratory drive including apnea, even at recommended dosages of Butalbital, Acetaminophen, Caffeine, and Codeine Phosphate Capsules [see Warnings and Precautions (5.2)].

Elderly, Cachectic, or Debilitated Patients: Life-threatening respiratory depression is more likely to occur in elderly, cachectic, or debilitated patients because they may have altered pharmacokinetics or altered clearance compared to younger, healthier patients [see Warnings and Precautions (5.2)].

Regularly evaluate such patients, particularly when initiating and titrating Butalbital, Acetaminophen, Caffeine, and Codeine Phosphate Capsules and when Butalbital, Acetaminophen, Caffeine, and Codeine Phosphate Capsules are given concomitantly with other drugs that depress respiration [see Warnings and Precautions (5.2), Drug Interactions (7)]. Alternatively, consider the use of non-opioid analgesics in these patients.

5.11 Interaction with Monoamine Oxidase Inhibitors

Monoamine oxidase inhibitors (MAOIs) may potentiate the effects of morphine, codeine’s active metabolite, including respiratory depression, coma, and confusion. Butalbital, Acetaminophen, Caffeine, and Codeine Phosphate Capsules should not be used in patients taking MAOIs or within 14 days of stopping such treatment.

5.12 Adrenal Insufficiency

Cases of adrenal insufficiency have been reported with opioid use, more often following greater than one month of use. Presentation of adrenal insufficiency may include non-specific symptoms and signs including nausea, vomiting, anorexia, fatigue, weakness, dizziness, and low blood pressure. If adrenal insufficiency is suspected, confirm the diagnosis with diagnostic testing as soon as possible. If adrenal insufficiency is diagnosed, treat with physiologic replacement doses of corticosteroids. Wean the patient off of the opioid to allow adrenal function to recover and continue corticosteroid treatment until adrenal function recovers. Other opioids may be tried as some cases reported use of a different opioid without recurrence of adrenal insufficiency. The information available does not identify any particular opioids as being more likely to be associated with adrenal insufficiency.

5.13 Severe Hypotension

Butalbital, Acetaminophen, Caffeine, and Codeine Phosphate Capsules may cause severe hypotension including orthostatic hypotension and syncope in ambulatory patients. There is increased risk in patients whose ability to maintain blood pressure has already been compromised by a reduced blood volume or concurrent administration of certain CNS depressant drugs (e.g., phenothiazines or general anesthetics) [see Drug Interactions (7)]. Regularly evaluate these patients for signs of hypotension after initiating or titrating the dosage of Butalbital, Acetaminophen, Caffeine, and Codeine Phosphate Capsules. In patients with circulatory shock, Butalbital, Acetaminophen, Caffeine, and Codeine Phosphate Capsules may cause vasodilation that can further reduce cardiac output and blood pressure. Avoid the use of Butalbital, Acetaminophen, Caffeine, and Codeine Phosphate Capsules in patients with circulatory shock.

5.14 Risks of Use in Patients with Increased Intracranial Pressure, Brain Tumors, Head Injury, or Impaired Consciousness

In patients who may be susceptible to the intracranial effects of CO2 retention (e.g., those with evidence of increased intracranial pressure or brain tumors), Butalbital, Acetaminophen, Caffeine, and Codeine Phosphate Capsules may reduce respiratory drive, and the resultant CO2 retention can further increase intracranial pressure. Monitor such patients for signs of sedation and respiratory depression, particularly when initiating therapy with Butalbital, Acetaminophen, Caffeine, and Codeine Phosphate Capsules.

Opioids may also obscure the clinical course in a patient with a head injury. Avoid the use of Butalbital, Acetaminophen, Caffeine, and Codeine Phosphate Capsules in patients with impaired consciousness or coma.

5.15 Risks of Gastrointestinal Complications

Butalbital, Acetaminophen, Caffeine, and Codeine Phosphate Capsules are contraindicated in patients with known or suspected gastrointestinal obstruction, including paralytic ileus.

The codeine in Butalbital, Acetaminophen, Caffeine, and Codeine Phosphate Capsules may cause spasm of the sphincter of Oddi. Opioids may cause increases in serum amylase. Regularly evaluate patients with biliary tract disease, including acute pancreatitis for worsening symptoms.

Cases of opioid-induced esophageal dysfunction (OIED) have been reported in patients taking opioids. The risk of OIED may increase as the dose and/or duration of opioids increases. Regularly evaluate patients for signs and symptoms of OIED (e.g., dysphagia, regurgitation, non-cardiac chest pain) and, if necessary, adjust opioid therapy as clinically appropriate [see Clinical Pharmacology (12.2)].

5.16 Hypersensitivity/Anaphylaxis

There have been post-marketing reports of hypersensitivity and anaphylaxis associated with the use of acetaminophen. Clinical signs included swelling of the face, mouth, and throat, respiratory distress, urticaria, rash, pruritus, and vomiting. There were infrequent reports of life-threatening anaphylaxis requiring emergency medical attention. Instruct patients to discontinue Butalbital, Acetaminophen, Caffeine, and Codeine Phosphate Capsules immediately and seek medical care if they experience these symptoms. Do not prescribe Butalbital, Acetaminophen, Caffeine, and Codeine Phosphate Capsules for patients with acetaminophen allergy.

5.17 Increased Risk of Seizures in Patients with Seizure Disorders

The codeine in Butalbital, Acetaminophen, Caffeine, and Codeine Phosphate Capsules may increase the frequency of seizures in patients with seizure disorders and may increase the risk of seizures occurring in other clinical settings associated with seizures.

Regularly evaluate patients with a history of seizure disorders for worsened seizure control during Butalbital, Acetaminophen, Caffeine, and Codeine Phosphate Capsules therapy.

5.18 Withdrawal

Do not rapidly reduce or abruptly discontinue Butalbital, Acetaminophen, Caffeine, and Codeine in a patient physically dependent on opioids. Rapid tapering of Butalbital, Acetaminophen, Caffeine, and Codeine in a patient physically dependent on opioids may lead to a withdrawal syndrome and return of pain [see Dosage and Administration (2.5), Drug Abuse and Dependence (9.3)].

Additionally, avoid the use of mixed agonist/antagonist (e.g., pentazocine, nalbuphine, and butorphanol) or partial agonist (e.g., buprenorphine) analgesics in patients who are receiving a full opioid agonist analgesic, including Butalbital, Acetaminophen, Caffeine, and Codeine Phosphate Capsules. In these patients, mixed agonist/antagonist and partial agonist analgesics may reduce the analgesic effect and/or precipitate withdrawal symptoms.

When discontinuing Butalbital, Acetaminophen, Caffeine, and Codeine Phosphate Capsules, in a physically-dependent patient, gradually taper the dosage [see Dosage and Administration (2.5)]. Abrupt discontinuation of butalbital can cause seizures [see Drug Abuse and Dependence (9.3)].

5.19 Risks of Driving and Operating Machinery

Butalbital, Acetaminophen, Caffeine, and Codeine Phosphate Capsules may impair the mental or physical abilities needed to perform potentially hazardous activities such as driving a car or operating machinery. Warn patients not to drive or operate dangerous machinery unless they are tolerant to the effects of Butalbital, Acetaminophen, Caffeine, and Codeine Phosphate Capsules and know how they will react to the medication.

5.20 Serious Skin Reactions

Rarely, acetaminophen may cause serious skin reactions such as acute generalized exanthematous pustulosis (AGEP), Stevens-Johnson Syndrome (SJS), and toxic epidermal necrolysis (TEN), which can be fatal. Patients should be informed about the signs of serious skin reactions, and use of the drug should be discontinued at the first appearance of skin rash or any other sign of hypersensitivity.

5.21 Drug/Laboratory Test Interactions

Codeine: Codeine may increase serum amylase levels.

Acetaminophen: Acetaminophen may produce false positive test results for urinary 5‑hydroxyindoleacetic acid.

6 ADVERSE REACTIONS

The following serious adverse reactions are described, or described in greater detail, in other sections:

- Addiction, Abuse, and Misuse [see Warnings and Precautions (5.1)]
- Life-Threatening Respiratory Depression [see Warnings and Precautions (5.2)]
- Interactions with Benzodiazepines and other CNS Depressants [see Warnings and Precautions (5.3)]
- Neonatal Opioid Withdrawal Syndrome [see Warnings and Precautions (5.4)]
- Ultra-Rapid Metabolism of Codeine and Other Risk Factors for Life-Threatening Respiratory Depression in Children [see Warnings and Precautions (5.6)]
- Hepatotoxicity [see Warnings and Precautions (5.8)]
- Opioid-Induced Hyperalgesia and Allodynia [see Warnings and Precautions (5.9)]
- Adrenal Insufficiency [see Warnings and Precautions (5.12)]
- Severe Hypotension [see Warnings and Precautions (5.13)]
- Gastrointestinal Adverse Reactions [see Warnings and Precautions (5.15)]
- Anaphylaxis [see Warnings and Precautions (5.16)]
- Seizures [see Warnings and Precautions (5.17)]
- Withdrawal [see Warnings and Precautions (5.18)]
- Serious Skin Reactions [see Warnings and Precautions (5.20)]

The following adverse reactions associated with the use of butalbital, acetaminophen, caffeine, and codeine phosphate were identified in clinical studies or post-marketing reports. Because some of these reactions were reported voluntarily from a population of uncertain size, it is not always possible to reliably estimate their frequency or establish a causal relationship to drug exposure.

Frequently Observed

The most frequently reported adverse reactions were drowsiness, lightheadedness, dizziness, sedation, shortness of breath, nausea, vomiting, abdominal pain, and intoxicated feeling.

Infrequently Observed

All adverse events tabulated below are classified as infrequent.

Central Nervous: headache, shaky feeling, tingling, agitation, fainting, fatigue, heavy eyelids, high energy, hot spells, numbness, sluggishness, seizure. Mental confusion, excitement or depression can also occur due to intolerance, particularly in elderly or debilitated patients, or due to overdosage of butalbital.

Autonomic Nervous: dry mouth, hyperhidrosis.

Gastrointestinal: difficulty swallowing, heartburn, flatulence, constipation.

Cardiovascular: tachycardia.

Musculoskeletal: leg pain, muscle fatigue.

Genitourinary: diuresis.

Miscellaneous: pruritus, fever, earache, nasal congestion, tinnitus, euphoria, allergic reactions.

The following adverse reactions have been voluntarily reported as temporally associated with Butalbital, Aspirin, Caffeine, and Codeine Phosphate Capsules, a related product containing aspirin, butalbital, caffeine, and codeine phosphate.

Central Nervous: abuse, addiction, anxiety, disorientation, hallucination, hyperactivity, insomnia, libido decrease, nervousness, neuropathy, psychosis, sexual activity increase, slurred speech, twitching, unconsciousness, vertigo.

Autonomic Nervous: epistaxis, flushing, miosis, salivation.

Gastrointestinal: anorexia, appetite increased, diarrhea, esophagitis, gastroenteritis, gastrointestinal spasms, hiccup, mouth burning, pyloric ulcer.

Cardiovascular: chest pain, hypotensive reaction, palpitations, syncope.

Skin: erythema, erythema multiforme, exfoliative dermatitis, hives, rash, toxic epidermal necrolysis.

Urinary: kidney impairment, urinary difficulty.

Miscellaneous: allergic reaction, anaphylactic shock, cholangiocarcinoma, drug interaction with erythromycin (stomach upset), edema.

The following adverse reactions have been reported with the components of Butalbital, Acetaminophen, Caffeine, and Codeine Phosphate Capsules. Potential effects of high dosage are listed in the OVERDOSAGE section.

Acetaminophen: allergic reactions, rash, thrombocytopenia, agranulocytosis.

Caffeine: cardiac stimulation, irritability, tremor, dependence, nephrotoxicity, hyperglycemia.

Codeine: nausea, vomiting, drowsiness, lightheadedness, constipation, pruritus.

Several cases of dermatological reactions, including toxic epidermal necrolysis and erythema multiforme, have been reported for butalbital, acetaminophen, and caffeine tablets, USP.

Serotonin syndrome: Cases of serotonin syndrome, a potentially life-threatening condition, have been reported during concomitant use of opioids with serotonergic drugs.

Adrenal insufficiency: Cases of adrenal insufficiency have been reported with opioid use, more often following greater than one month of use.

Androgen deficiency: Cases of androgen deficiency have occurred with use of opioids for an extended period of time [see Clinical Pharmacology (12.2)].

Hyperalgesia and Allodynia: Cases of hyperalgesia and allodynia have been reported with opioid therapy of any duration [see Warnings and Precautions (5.9)].

Hypoglycemia: Cases of hypoglycemia have been reported in patients taking opioids. Most reports were in patients with at least one predisposing risk factor (e.g., diabetes).

Opioid-induced esophageal dysfunction (OIED): Cases of OIED have been reported in patients taking opioids and may occur more frequently in patients taking higher doses of opioids, and/or in patients taking opioids longer term [see Warnings and Precautions (5.15)].

Adverse Reactions from Observational Studies

A prospective, observational cohort study estimated the risks of addiction, abuse, and misuse in patients initiating long-term use of Schedule II opioid analgesics between 2017 and 2021. Study participants included in one of more analyses had been enrolled in selected insurance plans or health systems for at least one year, were free of at least one outcome at baseline, completed a minimum number of follow-up assessments, and either: 1) filled multiple extended-release/long-acting opioid analgesic prescriptions during a 90-day period (n=978); or 2) filled any Schedule II opioid analgesic prescriptions covering at least 70 of 90 days (n=1,244). Those included also had no dispensing of the qualifying opioids in the previous 6 months.

Over 12 months:

- approximately 1% to 6% of participants across the two cohorts newly met criteria for addiction, as assessed with two validated interview-based measures of moderate-to-severe opioid use disorder based on Diagnostic and Statistical Manual of Mental Disorders, Fifth Edition (DSM-5) criteria, and
- approximately 9% and 22% of participants across the two cohorts newly met criteria for prescription opioid abuse and misuse [defined in Drug Abuse and Dependence (9.2)], respectively, as measured with a validated self-reported instrument.

A retrospective, observational cohort study estimated the risk of opioid-involved overdose or opioid overdose-related death in patients with new long-term use of Schedule II opioid analgesics from 2006 through 2016 (n=220,249). Included patients had been enrolled in either one of two commercial insurance programs, one managed care program, or one Medicaid program for at least 9 months. New long-term use was defined as having Schedule II opioid analgesic prescriptions covering at least 70 days’ supply over the 3 months prior to study entry and none during the preceding 6 months. Patients were excluded if they had an opioid-involved overdose in the 9 months prior to study entry. Overdose was measured using a validated medical code-based algorithm with linkage to the National Death Index database. The 5-year cumulative incidence estimates for opioid-involved overdose or opioid overdose-related death ranged from approximately 1.5% to 4% across study sites, counting only the first event during follow-up. Approximately 17% of first opioid overdoses observed over the entire study period (5-11 years, depending on the study site) were fatal. Higher baseline opioid dose was the strongest and most consistent predictor of opioid-involved overdose or opioid overdose-related death. Study exclusion criteria may have selected patients at lower risk of overdose, and substantial loss to follow-up (approximately 80%) also may have biased estimates.

The risk estimates from the studies described above may not be generalizable to all patients receiving opioid analgesics, such as those with exposures shorter or longer than the duration evaluated in the studies.

7 DRUG INTERACTIONS

Table 1 includes clinically significant drug interactions with Butalbital, Acetaminophen, Caffeine, and Codeine Phosphate Capsules.

Table 1: Clinically Significant Drug Interactions with Butalbital, Acetaminophen, Caffeine, and Codeine Phosphate Capsules

Inhibitors of CYP3A4
Clinical Impact: | The concomitant use of Butalbital, Acetaminophen, Caffeine, and Codeine Phosphate Capsules with CYP3A4 inhibitors may result in an increase in codeine plasma concentrations with subsequently greater metabolism by cytochrome CYP2D6, resulting in greater morphine levels, which could increase or prolong adverse reactions and may cause potentially fatal respiratory depression, particularly when an inhibitor is added after a stable dose of Butalbital, Acetaminophen, Caffeine, and Codeine Phosphate Capsules is achieved [see Warnings and Precautions (5.7)].; After stopping a CYP3A4 inhibitor, as the effects of the inhibitor decline, it may result in lower codeine levels, greater norcodeine levels, and less metabolism via 2D6 with resultant lower morphine levels [see Clinical Pharmacology (12.3)], resulting in decreased opioid efficacy or a withdrawal syndrome in patients who had developed physical dependence to codeine.
Intervention: | If concomitant use with CYP3A4 inhibitor is necessary, consider dosage reduction of Butalbital, Acetaminophen, Caffeine, and Codeine Phosphate Capsules until stable drug effects are achieved. Evaluate patients at frequent intervals for respiratory depression and sedation.; If a CYP3A4 inhibitor is discontinued, consider increasing the Butalbital, Acetaminophen, Caffeine, and Codeine Phosphate Capsules dosage until stable drug effects are achieved. Evaluate for signs of opioid withdrawal.
Examples: | Macrolide antibiotics (e.g., erythromycin), azole-antifungal agents (e.g., ketoconazole), protease inhibitors (e.g., ritonavir), grapefruit juice
CYP3A4 Inducers
Clinical Impact: | The concomitant use of Butalbital, Acetaminophen, Caffeine, and Codeine Phosphate Capsules and CYP3A4 inducers can result in lower codeine levels, greater norcodeine levels, and less metabolism via 2D6 with resultant lower morphine levels [see Clinical Pharmacology (12.3)], resulting in decreased efficacy or onset of a withdrawal syndrome in patients who have developed physical dependence [see Warnings and Precautions (5.7)].; After stopping a CYP3A4 inducer, as the effects of the inducer decline, the codeine plasma concentration may increase with subsequently greater metabolism by cytochrome CYP2D6, resulting in greater morphine levels [see Clinical Pharmacology (12.3)], which could increase or prolong both the therapeutic effects and adverse reactions, and may cause serious respiratory depression.
Intervention: | If concomitant use of a CYP3A4 inducer is necessary, evaluate the patient at frequent intervals for reduced efficacy and signs of opioid withdrawal and consider increasing the Butalbital, Acetaminophen, Caffeine, and Codeine Phosphate Capsules dosage as needed.; If a CYP3A4 inducer is discontinued, consider lowering Butalbital, Acetaminophen, Caffeine, and Codeine Phosphate Capsules dosage until stable drug effects are achieved. Evaluate patients at frequent intervals for signs of respiratory depression and sedation.
Examples: | Rifampin, carbamazepine, phenytoin
Inhibitors of CYP2D6
Clinical Impact: | Codeine is metabolized by CYP2D6 to form morphine. The concomitant use of Butalbital, Acetaminophen, Caffeine, and Codeine Phosphate Capsules and CYP2D6 inhibitors can increase the plasma concentration of codeine, but can decrease the plasma concentrations of active metabolite morphine, which could result in reduced analgesic efficacy or symptoms of opioid withdrawal, particularly when an inhibitor is added after a stable dose of Butalbital, Acetaminophen, Caffeine, and Codeine Phosphate Capsules is achieved [see Clinical Pharmacology (12.3)].; After stopping a CYP2D6 inhibitor, as the effects of the inhibitor decline, the codeine plasma concentration will decrease but the active metabolite morphine plasma concentration will increase, which could increase or prolong adverse reactions and may cause potentially fatal respiratory depression [see Clinical Pharmacology (12.3)].
Intervention: | If concomitant use with a CYP2D6 inhibitor is necessary, or if a CYP2D6 inhibitor is discontinued after concomitant use, consider dosage adjustment of Butalbital, Acetaminophen, Caffeine, and Codeine Phosphate Capsules and evaluate patients at frequent intervals.; If concomitant use with CYP2D6 inhibitors is necessary, evaluate the patient for reduced efficacy or signs and symptoms of opioid withdrawal and consider increasing the dosage of Butalbital, Acetaminophen, Caffeine, and Codeine Phosphate Capsules as needed.; After stopping use of a CYP2D6 inhibitor, consider reducing the dosage of Butalbital, Acetaminophen, Caffeine, and Codeine Phosphate Capsules and evaluate the patient at frequent intervals for signs and symptoms of respiratory depression or sedation.
Examples: | paroxetine, fluoxetine, bupropion, quinidine
Benzodiazepines and Other Central Nervous System (CNS) Depressants
Clinical Impact: | Due to additive pharmacologic effect, the concomitant use of benzodiazepines or other CNS depressants, including alcohol, can increase the risk of hypotension, respiratory depression, profound sedation, coma, and death.
Intervention: | Reserve concomitant prescribing of these drugs for use in patients for whom alternative treatment options are inadequate. Limit dosages and durations to the minimum required. Inform patients and caregivers of this potential interaction and educate them on the signs and symptoms of respiratory depression (including sedation). If concomitant use is warranted, consider recommending or prescribing an opioid overdose reversal agent [see Dosage and Administration (2.2), Warnings and Precautions (5.1, 5.2, 5.3)].
Examples: | Benzodiazepines and other sedatives/hypnotics, anxiolytics, tranquilizers, muscle relaxants, general anesthetics, antipsychotics, gabapentinoids (gabapentin or pregabalin), other opioids, alcohol.
Serotonergic Drugs
Clinical Impact: | The concomitant use of opioids with other drugs that affect the serotonergic neurotransmitter system has resulted in serotonin syndrome.
Intervention: | If concomitant use is warranted, frequently evaluate the patient, particularly during treatment initiation and dose adjustment. Discontinue Butalbital, Acetaminophen, Caffeine, and Codeine Phosphate Capsules if serotonin syndrome is suspected.
Examples: | Selective serotonin reuptake inhibitors (SSRIs), serotonin and norepinephrine reuptake inhibitors (SNRIs), tricyclic antidepressants (TCAs), triptans, 5-HT3 receptor antagonists, drugs that affect the serotonin neurotransmitter system (e.g., mirtazapine, trazodone, tramadol), certain muscle relaxants (i.e., cyclobenzaprine, metaxalone), monoamine oxidase (MAO) inhibitors (those intended to treat psychiatric disorders and also others, such as linezolid and intravenous methylene blue).
Monoamine Oxidase Inhibitors (MAOIs)
Clinical Impact: | MAOI interactions with opioids may manifest as serotonin syndrome or opioid toxicity (e.g., respiratory depression, coma) [see Warnings and Precautions (5.11)].
Intervention: | Do not use Butalbital, Acetaminophen, Caffeine, and Codeine Phosphate Capsules in patients taking MAOIs or within 14 days of stopping such treatment.; If urgent use of an opioid is necessary, use test doses and frequent titration of small doses of other opioids (such as oxycodone, hydrocodone, oxymorphone, hydromorphone, or buprenorphine) to treat pain while closely monitoring blood pressure and signs and symptoms of CNS and respiratory depression.
Examples: | phenelzine, tranylcypromine, linezolid
Mixed Agonist/Antagonist and Partial Agonist Opioid Analgesics
Clinical Impact: | May reduce the analgesic effect of Butalbital, Acetaminophen, Caffeine, and Codeine Phosphate Capsules and/or precipitate withdrawal symptoms.
Intervention: | Avoid concomitant use.
Examples: | butorphanol, nalbuphine, pentazocine, buprenorphine
Muscle Relaxants
Clinical Impact: | Codeine may enhance the neuromuscular blocking action of skeletal muscle relaxants and produce an increased degree of respiratory depression.
Intervention: | Because respiratory depression may be greater than otherwise expected, decrease the dosage of Butalbital, Acetaminophen, Caffeine, and Codeine Phosphate Capsules and/or the muscle relaxant as necessary. Due to the risk of respiratory depression with concomitant use of skeletal muscle relaxants and opioids, consider recommending or prescribing an opioid overdose reversal agent [see Dosage and Administration (2.2), Warnings and Precautions (5.2, 5.3)].
Examples: | cyclobenzaprine, metaxalone
Diuretics
Clinical Impact: | Opioids can reduce the efficacy of diuretics by inducing the release of antidiuretic hormone.
Intervention: | Evaluate patients for signs of diminished diuresis and/or effects on blood pressure and increase the dosage of the diuretic as needed.
Anticholinergic Drugs
Clinical Impact: | The concomitant use of anticholinergic drugs may increase risk of urinary retention and/or severe constipation, which may lead to paralytic ileus.
Intervention: | Evaluate patients for signs of urinary retention or reduced gastric motility when Butalbital, Acetaminophen, Caffeine, and Codeine Phosphate Capsules are used concomitantly with anticholinergic drugs.

8 USE IN SPECIFIC POPULATIONS

8.1 Pregnancy

Risk Summary

Use of opioid analgesics for an extended period of time during pregnancy may cause neonatal opioid withdrawal syndrome [see Warnings and Precautions (5.4)]. Available data with Butalbital, Acetaminophen, Caffeine, and Codeine Phosphate Capsules in pregnant women are insufficient to inform a drug-associated risk for major birth defects and miscarriage. There are risks to the mother and infant associated with use of Butalbital, Acetaminophen, Caffeine, and Codeine Phosphate Capsules for an extended period of time during pregnancy (see Clinical Considerations).

Animal reproduction studies have not been conducted with the combination of Butalbital, Acetaminophen, Caffeine, and Codeine Phosphate Capsules or with butalbital alone. In animal reproduction studies, codeine administration during organogenesis has been shown to produce delayed ossification in the offspring of mice at 2.8 times maximum recommended human dose (MRHD) of 180 mg/day, embryolethal and fetotoxic effects in the offspring of rats and hamsters at approximately 4 to 6 times the MRHD, and cranial malformations/cranioschisis in the offspring of hamsters between 2 and 8 times the MRHD. Reproductive and developmental studies in rats and mice from the published literature identified adverse events at clinically relevant doses with acetaminophen. Treatment of pregnant rats with doses of acetaminophen approximately 2 times the maximum human daily dose (MHDD) showed evidence of fetotoxicity and increases in bone variations in the fetuses. In another study, necrosis was observed in the liver and kidney of both pregnant rats and fetuses at doses approximately 2 times the MHDD. In mice treated with acetaminophen at doses within the clinical dosing range, cumulative adverse effects on reproduction were seen in a continuous breeding study. A reduction in number of litters of the parental mating pair was observed as well as retarded growth and abnormal sperm in their offspring and reduced birth weight in the next generation [see Data].

The background risk of major birth defects and miscarriage for the indicated population is unknown. All pregnancies have a background risk of birth defect, loss, or other adverse outcomes. In the U.S. general population, the estimated background risk of major birth defects and miscarriage in clinically recognized pregnancies is 2 to 4% and 15 to20%, respectively.

Clinical Considerations

Fetal/Neonatal Adverse Reactions

Use of opioid analgesics for an extended period of time during pregnancy for medical or nonmedical purposes can result in physical dependence in the neonate and neonatal opioid withdrawal syndrome shortly after birth.

Neonatal opioid withdrawal syndrome presents as irritability, hyperactivity and abnormal sleep pattern, high pitched cry, tremor, vomiting, diarrhea and failure to gain weight. The onset, duration, and severity of neonatal opioid withdrawal syndrome vary based on the specific opioid used, duration of use, timing and amount of last maternal use, and rate of elimination of the drug by the newborn. Observe newborns for symptoms of neonatal opioid withdrawal syndrome and manage accordingly [see Warnings and Precautions (5.4)].

Labor or Delivery

Use of codeine during labor may lead to respiratory depression in the neonate.

Opioids cross the placenta and may produce respiratory depression and psycho-physiologic effects in neonates. An opioid overdose reversal agent, such as naloxone or nalmefene, must be available for reversal of opioid-induced respiratory depression in the neonate. Butalbital, Acetaminophen, Caffeine, and Codeine Phosphate Capsules are not recommended for use in pregnant women during or immediately prior to labor, when other analgesic techniques are more appropriate. Opioid analgesics, including Butalbital, Acetaminophen, Caffeine, and Codeine Phosphate Capsules, can prolong labor through actions which temporarily reduce the strength, duration, and frequency of uterine contractions. However, this effect is not consistent and may be offset by an increased rate of cervical dilation, which tends to shorten labor. Monitor neonates exposed to opioid analgesics during labor for signs of excess sedation and respiratory depression.

Data

Human Data

Published data from a large population-based prospective cohort study and a population-based, case-control study do not clearly report an association with oral acetaminophen and major birth defects, miscarriage, or adverse maternal or fetal outcomes when acetaminophen is used during pregnancy. However, these studies cannot definitely establish the absence of any risk because of methodological limitations including recall bias.

Withdrawal seizures were reported in a two-day-old male infant whose mother had taken a butalbital containing drug during the last 2 months of pregnancy. Butalbital was found in the infant's serum. The infant was given phenobarbital 5 mg/kg, which was tapered without further seizure or other withdrawal symptoms.

Animal Data

Animal reproduction studies have not been conducted with Butalbital, Acetaminophen, Caffeine, and Codeine Phosphate Capsules or with butalbital alone.

The following data are based on findings from studies performed with either codeine or acetaminophen alone.

Codeine

In a study in which pregnant hamsters were administered 150 mg/kg twice daily of codeine (oral; approximately 14 times the maximum recommended daily dose of 180 mg/day for adults on a mg/m^2 basis) during organogenesis cranial malformations (i.e., meningoencephalocele) in several fetuses were reported; as well as the observation of increases in the percentage of resorptions per litter. Doses of 50 and 150 mg/kg, bid resulted in fetotoxicity as demonstrated by decreased fetal body weight. In an earlier study in hamsters, single oral doses of 73 to 360 mg/kg level on Gestation Day 8 (oral; approximately 4 to 16 times the maximum recommended daily dose of 180 mg/day for adults on a mg/m^2 basis), reportedly produced cranioschisis in all of the fetuses examined.

In studies in rats, doses at the 120 mg/kg level (oral; approximately 6 times the maximum recommended daily dose of 180 mg/day for adults on a mg/m^2 basis) during organogenesis, in the toxic range for the adult animal, were associated with an increase in embryo resorption at the time of implantation.

In pregnant mice, a single 100 mg/kg dose (subcutaneous; approximately 2.8 times the recommended daily dose of 180 mg/day for adults on a mg/mg^2 basis) administered between Gestation Day 7 and 12 reportedly resulted in delayed ossification in the offspring.

No teratogenic effects were observed in rabbits administered up to 30 mg/kg (approximately 4 times the maximum recommended daily dose of 180 mg/day for adults on a mg/m^2 basis) of codeine during organogenesis.

Codeine (30 mg/kg) administered subcutaneously to pregnant rats during pregnancy and for 25 days after delivery increased neonatal mortality at birth. This dose is 1.6 times the maximum recommended human dose of 180 mg/day on a body surface area comparison.

Acetaminophen

Studies in pregnant rats that received oral acetaminophen during organogenesis at doses up to 1.7 the maximum human daily dose (MHDD) of 1950 mg/day based on a body surface area comparison showed evidence of fetotoxicity (reduced fetal weight and length) and a dose-related increase in bone variations (reduced ossification and rudimentary rib changes). Offspring had no evidence of external, visceral, or skeletal malformations. When pregnant rats received oral acetaminophen throughout gestation at doses of 2.4 times the MHDD (based on a body surface area comparison), areas of necrosis occurred in both the liver and kidney of pregnant rats and fetuses. These effects did not occur in animals that received oral acetaminophen at doses 0.6 times the MHDD, based on a body surface area comparison. In a continuous breeding study, pregnant mice received 0.25, 0.5, or 1.0% acetaminophen via the diet (357, 715, or 1430 mg/kg/day). These doses are approximately 0.86, 1.7, and 3.4 times the MHDD, respectively, based on a body surface area comparison. A dose-related reduction in body weights of fourth and fifth litter offspring of the treated mating pair occurred during lactation and post-weaning at all doses. Animals in the high dose group had a reduced number of litters per mating pair, male offspring with an increased percentage of abnormal sperm, and reduced birth weights in the next generation pups.

Caffeine

In studies performed in adult animals, caffeine (as caffeine base) administered to pregnant mice as sustained release pellets at 50 mg/kg (less than the maximum recommended daily dose on a mg/m^2 basis), during the period of organogenesis, caused a low incidence of cleft palate and exencephaly in the fetuses.

8.2 Lactation

Risk Summary

Codeine and its active metabolite, morphine, are present in human milk. There are published studies and cases that have reported excessive sedation, respiratory depression, and death in infants exposed to codeine via breast milk. Women who are ultra-rapid metabolizers of codeine achieve higher than expected serum levels of morphine, potentially leading to higher levels of morphine in breast milk that can be dangerous in their breastfed infants. In women with normal codeine metabolism (normal CYP2D6 activity), the amount of codeine secreted into human milk is low and dose dependent.

There is no information on the effects of the codeine on milk production. Because of the potential for serious adverse reactions, including excess sedation, respiratory depression, and death in a breastfed infant, advise patients that breastfeeding is not recommended during treatment with Butalbital, Acetaminophen, Caffeine, and Codeine Phosphate Capsules [see Warnings and Precautions (5.6)].

Acetaminophen is present in human milk in small quantities after oral administration. Based on data from more than 15 nursing mothers, the calculated infant daily dose of acetaminophen is approximately 1 to 2% of the maternal dose. There is one well-documented report of a rash in a breastfed infant that resolved when the mother stopped acetaminophen use and recurred when she resumed acetaminophen use.

Barbiturates and caffeine are also excreted in breast milk in small amounts. Because of potential for serious adverse reactions in nursing infants from Butalbital, Acetaminophen, Caffeine, and Codeine Phosphate Capsules, a decision should be made whether to discontinue nursing or to discontinue the drug, taking into account the importance of the drug to the mother.

Clinical Considerations

If infants are exposed to Butalbital, Acetaminophen, Caffeine, and Codeine Phosphate Capsules through breast milk, they should be monitored for excess sedation and respiratory depression. Withdrawal symptoms can occur in breastfed infants when maternal administration of an opioid analgesic is stopped, or when breastfeeding is stopped.

8.3 Females and Males of Reproductive Potential

Infertility

Use of opioids for an extended period of time may cause reduced fertility in females and males of reproductive potential. It is not known whether these effects on fertility are reversible [see Adverse Reactions (6), Clinical Pharmacology (12.2), Nonclinical Pharmacology (13.1)].

Published literature indicates that acetaminophen affects sperm development in mice with consequent reduction in litter size in a multigeneration study [see Nonclinical Toxicology (13.1)].

8.4 Pediatric Use

The safety and effectiveness of Butalbital, Acetaminophen, Caffeine, and Codeine Phosphate Capsules in pediatric patients have not been established.

Life-threatening respiratory depression and deaths have occurred in children who received codeine [see Warnings and Precautions (5.6)]. In most of the reported cases, these events followed tonsillectomy and/or adenoidectomy, and many of the children had evidence of being ultra-rapid metabolizers of codeine (i.e., multiple copies of the gene for cytochrome P450 isoenzyme 2D6 or high morphine concentrations). Children with sleep apnea may be particularly sensitive to the respiratory depressant effects of codeine. Because of the risk of life-threatening respiratory depression and death:

- Butalbital, Acetaminophen, Caffeine, and Codeine Phosphate Capsules are contraindicated for all children younger than 12 years of age [see Contraindications (4)].
- Butalbital, Acetaminophen, Caffeine, and Codeine Phosphate Capsules are contraindicated for post-operative management in pediatric patients younger than 18 years of age following tonsillectomy and/or adenoidectomy [see Contraindications (4)].
- Avoid the use of Butalbital, Acetaminophen, Caffeine, and Codeine Phosphate Capsules in adolescents 12 to 18 years of age who have other risk factors that may increase their sensitivity to the respiratory depressant effects of codeine unless the benefits outweigh the risks. Risk factors include conditions associated with hypoventilation, such as post-operative status, obstructive sleep apnea, obesity, severe pulmonary disease, neuromuscular disease, and concomitant use of other medications that cause respiratory depression [see Warnings and Precautions (5.6)].

8.5 Geriatric Use

Clinical studies of Butalbital, Acetaminophen, Caffeine, and Codeine Phosphate Capsules did not include sufficient numbers of subjects aged 65 and over to determine whether they respond differently from younger subjects. Other reported clinical experience has not identified differences in responses between the elderly and younger patients. In general, dose selection for an elderly patient should be cautious, usually starting at the low end of the dosing range, reflecting the greater frequency of decreased hepatic, renal, or cardiac function, and of concomitant disease or other drug therapy.

Butalbital is known to be substantially excreted by the kidney, and the risk of toxic reactions to this drug may be greater in patients with impaired renal function. Because elderly patients are more likely to have decreased renal function, care should be taken in dose selection, and it may be useful to monitor renal function.

Elderly patients (aged 65 years or older) may have increased sensitivity to Butalbital, Acetaminophen, Caffeine, and Codeine Phosphate Capsules. In general, use caution when selecting a dosage for an elderly patient, usually starting at the low end of the dosing range, reflecting the greater frequency of decreased hepatic, renal, or cardiac function and of concomitant disease or other drug therapy.

Respiratory depression is the chief risk for elderly patients treated with opioids and has occurred after large initial doses were administered to patients who were not opioid-tolerant or when opioids were co-administered with other agents that depress respiration. Titrate the dosage of Butalbital, Acetaminophen, Caffeine, and Codeine Phosphate Capsules slowly in geriatric patients and frequently reevaluate the patient for signs of respiratory depression [see Warnings and Precautions (5.10)].

Components of this product are known to be substantially excreted by the kidney, and the risk of adverse reactions to this drug may be greater in patients with impaired renal function. Because elderly patients are more likely to have decreased renal function, care should be taken in dose selection, and it may be useful to regularly evaluate renal function.

8.6 Hepatic Impairment

No formal studies have been conducted in patients with hepatic impairment so the pharmacokinetics of butalbital, codeine, and acetaminophen in this patient population are unknown. Start these patients cautiously with lower doses of codeine sulfate or with longer dosing intervals and titrate slowly while regularly evaluating for side effects.

8.7 Renal Impairment

Codeine pharmacokinetics may be altered in patients with renal failure. Clearance may be decreased and the metabolites may accumulate to much higher plasma levels in patients with renal failure as compared to patients with normal renal function. Start these patients cautiously with lower doses of codeine sulfate or with longer dosing intervals and titrate slowly while carefully regularly evaluating for side effects. In patients with renal disease, regularly evaluate effects of therapy with serial renal function tests.

9 DRUG ABUSE AND DEPENDENCE

9.1 Controlled Substance

Butalbital, Acetaminophen, Caffeine, and Codeine Phosphate Capsules contain codeine. Codeine in combination with butalbital, acetaminophen, and caffeine is a Schedule III controlled substance.

9.2 Abuse

Butalbital, Acetaminophen, Caffeine, and Codeine Phosphate Capsules contains codeine, a substance with high potential for misuse and abuse, which can lead to the development of substance use disorder, including addiction [see Warnings and Precautions (5.1)].

Misuse is the intentional use, for therapeutic purposes, of a drug by an individual in a way other than prescribed by a healthcare provider or for whom it was not prescribed.

Abuse is the intentional, non-therapeutic use of a drug, even once, for its desirable psychological or physiological effects.

Drug addiction is a cluster of behavioral, cognitive, and physiological phenomena that may include a strong desire to take the drug, difficulties in controlling drug use (e.g., continuing drug use despite harmful consequences, giving a higher priority to drug use than other activities and obligations), and possible tolerance or physical dependence.

Misuse and abuse of Butalbital, Acetaminophen, Caffeine, and Codeine Phosphate Capsules increases risk of overdose, which may lead to central nervous system and respiratory depression, hypotension, seizures, and death. The risk is increased with concurrent abuse of Butalbital, Acetaminophen, Caffeine, and Codeine Phosphate Capsules with alcohol and/or other CNS depressants. Abuse of and addiction to opioids in some individuals may not be accompanied by concurrent tolerance and symptoms of physical dependence. In addition, abuse of opioids can occur in the absence of addiction.

All patients treated with opioids require careful and frequent reevaluation for signs of misuse, abuse, and addiction, because use of opioid analgesic products carries the risk of addiction even under appropriate medical use. Patients at high risk of Butalbital, Acetaminophen, Caffeine, and Codeine Phosphate Capsules abuse include those with a history of prolonged use of any opioid, including products containing codeine, those with a history of drug or alcohol abuse, or those who use Butalbital, Acetaminophen, Caffeine, and Codeine Phosphate Capsules in combination with other abused drugs.

“Drug-seeking” behavior is very common in persons with substance use disorders. Drug-seeking tactics include emergency calls or visits near the end of office hours, refusal to undergo appropriate examination, testing, or referral, repeated “loss” of prescriptions, tampering with prescriptions, and reluctance to provide prior medical records or contact information for other treating healthcare provider(s). “Doctor shopping” (visiting multiple prescribers to obtain additional prescriptions) is common among people who abuse drugs and people with substance use disorder. Preoccupation with achieving adequate pain relief can be appropriate behavior in a patient with inadequate pain control.

Butalbital, Acetaminophen, Caffeine, and Codeine Phosphate Capsules, like other opioids, can be diverted for nonmedical use into illicit channels of distribution. Careful record keeping of prescribing information, including quantity, frequency, and renewal requests, as required by state and federal law, is strongly advised.

Proper assessment of the patient, proper prescribing practices, periodic reevaluation of therapy, and proper dispensing and storage are appropriate measures that help to limit abuse of opioid drugs.

Risks Specific to Abuse of Butalbital, Acetaminophen, Caffeine, and Codeine Phosphate Capsules

Abuse of Butalbital, Acetaminophen, Caffeine, and Codeine Phosphate Capsules poses a risk of overdose and death. The risk is increased with concurrent use of Butalbital, Acetaminophen, Caffeine, and Codeine Phosphate Capsules with alcohol and/or other CNS depressants.

Butalbital, Acetaminophen, Caffeine, and Codeine Phosphate Capsules are approved for oral use only.

Parenteral drug abuse is commonly associated with transmission of infectious diseases such as hepatitis and HIV.

Butalbital

Barbiturates may be habit-forming: Tolerance, psychological dependence, and physical dependence may occur especially following prolonged use of high doses of barbiturates. The average daily dose for the barbiturate addict is usually about 1,500 mg. As tolerance to barbiturates develops, the amount needed to maintain the same level of intoxication increases; tolerance to a fatal dosage, however, does not increase more than twofold. As this occurs, the margin between an intoxication dosage and fatal dosage becomes smaller. The lethal dose of a barbiturate is far less if alcohol is also ingested. Major withdrawal symptoms (convulsions and delirium) may occur within 16 hours and last up to 5 days after abrupt cessation of these drugs. Intensity of withdrawal symptoms gradually declines over a period of approximately 15 days. Treatment of barbiturate dependence consists of cautious and gradual withdrawal of the drug. Barbiturate-dependent patients can be withdrawn by using a number of different withdrawal regimens. One method involves initiating treatment at the patient's regular dosage level and gradually decreasing the daily dosage as tolerated by the patient.

9.3 Dependence

Both tolerance and physical dependence can develop during use of opioid therapy.

Tolerance is a physiological state characterized by a reduced response to a drug after repeated administration (i.e., a higher dose of a drug is required to produce the same effect that was once obtained at a lower dose).

Physical dependence is a state that develops as a result of a physiological adaptation in response to repeated drug use, manifested by withdrawal signs and symptoms after abrupt discontinuation or a significant dose reduction of a drug.

Withdrawal may be precipitated through the administration of drugs with opioid antagonist activity (e.g., naloxone, nalmefene), mixed agonist/antagonist analgesics (e.g., pentazocine, butorphanol, nalbuphine), or partial agonists (e.g., buprenorphine). Physical dependence may not occur to a clinically significant degree until after several days to weeks of continued use.

Do not rapidly reduce or abruptly discontinue Butalbital, Acetaminophen, Caffeine, and Codeine Phosphate Capsules in a patient physically dependent on opioids. Rapid tapering of Butalbital, Acetaminophen, Caffeine, and Codeine Phosphate Capsules in a patient physically dependent on opioids may lead to serious withdrawal symptoms, uncontrolled pain, and suicide. Rapid discontinuation has also been associated with attempts to find other sources of opioid analgesics, which may be confused with drug-seeking for abuse.

When discontinuing Butalbital, Acetaminophen, Caffeine, and Codeine Phosphate Capsules gradually taper the dosage using a patient-specific plan that considers the following: the dose of Butalbital, Acetaminophen, Caffeine, and Codeine Phosphate Capsules the patient has been taking, the duration of treatment, and the physical and psychological attributes of the patient. To improve the likelihood of a successful taper and minimize withdrawal symptoms, it is important that the opioid tapering schedule is agreed upon by the patient. In patients taking opioids for an extended period of time at high doses, ensure that a multimodal approach to pain management, including mental health support (if needed), is in place prior to initiating an opioid analgesic taper [see Dosage and Administration (2.5), Warnings and Precautions (5.18)].

Infants born to mothers physically dependent on opioids will also be physically dependent and may exhibit respiratory difficulties and withdrawal signs [see Use in Specific Populations (8.1)].

10 OVERDOSAGE

Clinical Presentation

Acute overdose with codeine can be manifested by respiratory depression, somnolence progressing to stupor or coma, skeletal muscle flaccidity, cold and clammy skin, constricted pupils, and, in some cases, pulmonary edema, bradycardia, hypotension, hypoglycemia, partial or complete airway obstruction, atypical snoring, and death. Marked mydriasis rather than miosis may be seen with hypoxia in overdose situations [see Clinical Pharmacology (12.2)]. Toxic leukoencephalopathy has been reported after opioid overdose and can present hours, days, or weeks after apparent recovery from the initial intoxication.

Signs and Symptoms

Symptoms attributable to acute barbiturate poisoning include drowsiness, confusion, and coma; respiratory depression; hypotension; and hypovolemic shock.

Toxicity from codeine poisoning includes the opioid triad of: pinpoint pupils, depression of respiration, and loss of consciousness. Convulsions may occur.

In acetaminophen overdosage: dose dependent, potentially fatal hepatic necrosis is the most serious adverse effect. Renal tubular necrosis, hypoglycemic coma, and coagulation defects may also occur. Early symptoms following a potentially hepatotoxic overdose may include: nausea, vomiting, diaphoresis, and general malaise. Clinical and laboratory evidence of hepatic toxicity may not be apparent until 48 to 72 hours post-ingestion. Acute caffeine poisoning may cause insomnia, restlessness, tremor, and delirium, tachycardia, and extrasystoles.

Treatment of Overdose

In case of overdose, priorities are the re-establishment of a patent and protected airway and institution of assisted or controlled ventilation, if needed. Employ other supportive measures (including oxygen and vasopressors) in the management of circulatory shock and pulmonary edema as indicated. Cardiac arrest or arrhythmias will require advanced life-support measures.

For clinically significant respiratory or circulatory depression secondary to opioid overdose, administer an opioid overdose reversal agent such as naloxone or nalmefene.

Because the duration of opioid reversal is expected to be less than the duration of action of codeine in Butalbital, Acetaminophen, Caffeine, and Codeine Phosphate Capsules, carefully monitor the patient until spontaneous respiration is reliably re-established. If the response to an opioid overdose reversal agent is suboptimal or only brief in nature, administer additional reversal agent as directed by the product’s prescribing information.

In an individual physically dependent on opioids, administration of the recommended usual dosage of the opioid overdose reversal agent will precipitate an acute withdrawal syndrome. The severity of the withdrawal symptoms experienced will depend on the degree of physical dependence and the dose of the reversal agent administered. If a decision is made to treat serious respiratory depression in the physically dependent patient, administration of the reversal agent should be initiated with care and by titration with smaller than usual doses of the antagonist.

A single or multiple drug overdose with Butalbital, Acetaminophen, Caffeine, and Codeine Phosphate Capsules is a potentially lethal polydrug overdose, and consultation with a regional poison control center is recommended. Immediate treatment includes support of cardiorespiratory function and measures to reduce drug absorption. Oxygen, intravenous fluids, vasopressors, and other supportive measures should be employed as indicated. Assisted or controlled ventilation should also be considered. For respiratory depression due to overdosage or unusual sensitivity to codeine, parenteral naloxone is a specific and effective antagonist.

Gastric decontamination with activated charcoal should be administered just prior to N-acetylcysteine (NAC) to decrease systemic absorption if acetaminophen ingestion is known or suspected to have occurred within a few hours of presentation. Serum acetaminophen levels should be obtained immediately if the patient presents 4 hours or more after ingestion to assess potential risk of hepatotoxicity; acetaminophen levels drawn less than 4 hours post-ingestion may be misleading. To obtain the best possible outcome, NAC should be administered as soon as possible where impending or evolving liver injury is suspected. Intravenous NAC may be administered when circumstances preclude oral administration.

Vigorous supportive therapy is required in severe intoxication. Procedures to limit the continuing absorption of the drug must be readily performed since the hepatic injury is dose dependent and occurs early in the course of intoxication.

11 DESCRIPTION

Butalbital, Acetaminophen, Caffeine, and Codeine Phosphate Capsules are supplied in capsule form for oral administration. Each capsule contains:

Butalbital, USP…………..........50 mg

Acetaminophen, USP………...325 mg

Caffeine, USP……………........40 mg

Codeine phosphate, USP….......30 mg

Butalbital (5-allyl-5-isobutylbarbituric acid), is a short-to intermediate-acting barbiturate. It has the following structural formula:

Acetaminophen (4'hydroxyacetanilide), is a non-opiate, non-salicylate analgesic and antipyretic. It has the following structural formula:

Caffeine (1,3,7trimethylxanthine), a methylxanthine, is a central nervous system stimulant. It has the following structural formula:

Codeine phosphate (7,8-Didehydro-4,5α-epoxy-3-methoxy-17-methylmorphinan-6α-ol phosphate (1:1)(salt) hemihydrate) is an opioid agonist. It has the following structural formula:

Inactive Ingredients: colloidal silicon dioxide, magnesium stearate, pregelatinized starch. Gelatin

capsules contain D&C Red No. 33, FD&C Blue No. 1, gelatin, and titanium dioxide. The capsules are printed with edible inks containing D&C Red No. 7 Calcium Lake, FD&C Blue No. 1 Aluminum Lake, and titanium dioxide.

12 CLINICAL PHARMACOLOGY

12.1 Mechanism of Action

Butalbital, a barbiturate, is a GABAA receptor agonist and may inhibit excitatory AMPA receptors.

The precise mechanism of the analgesic properties of acetaminophen is not established but is thought to involve central actions.

Caffeine is a methylxanthine and CNS stimulant. The exact mechanism with respect to the indication is not clear; however, the effects of caffeine may be due to antagonism of adenosine receptors.

Codeine is an opioid agonist relatively selective for the mu-opioid receptor, but with a much weaker affinity than morphine. The analgesic properties of codeine have been speculated to come from its conversion to morphine, although the exact mechanism of analgesic action remains unknown.

12.2 Pharmacodynamics

Effects on the Central Nervous System

Butalbital, a barbiturate, is a central nervous system (CNS) depressant that can produce sedation, respiratory depression, and euphoria. The potential impact of butalbital on painful stimuli is not clear and in some individuals barbiturates may increase reaction to painful stimuli.

Codeine produces respiratory depression by direct action on brain stem respiratory centers. The respiratory depression involves a reduction in the responsiveness of the brain stem respiratory centers to both increases in carbon dioxide tension and to electrical stimulation.

Codeine causes miosis, even in total darkness. Pinpoint pupils are a sign of opioid overdose but are not pathognomonic (e.g., pontine lesions of hemorrhagic or ischemic origins may produce similar findings). Marked mydriasis rather than miosis may be seen due to hypoxia in overdose situations.

Acetaminophen has been shown to have analgesic activity in animal and human studies.

Effects on the Gastrointestinal Tract and Other Smooth Muscle

Codeine causes a reduction in motility associated with an increase in smooth muscle tone in the antrum of the stomach and duodenum. Digestion of food in the small intestine is delayed and propulsive contractions are decreased. Propulsive peristaltic waves in the colon are decreased, while tone may be increased to the point of spasm resulting in constipation. Other opioid-induced effects may include a reduction in biliary and pancreatic secretions, spasm of sphincter of Oddi, transient elevations in serum amylase, and opioid-induced esophageal dysfunction (OIED).

Effects on the Cardiovascular System

Butalbital may decrease blood pressure and heart rate when administered at sedative and hypnotic doses.

Codeine produces peripheral vasodilation which may result in orthostatic hypotension or syncope. Manifestations of histamine release and/or peripheral vasodilation may include pruritus, flushing, red eyes and sweating and/or orthostatic hypotension.

Effects on the Endocrine System

Opioids inhibit the secretion of adrenocorticotropic hormone (ACTH), cortisol, and luteinizing hormone (LH) in humans [see Adverse Reactions (6)]. They also stimulate prolactin, growth hormone (GH) secretion, and pancreatic secretion of insulin and glucagon.

Use of opioids for an extended period of time may influence the hypothalamic-pituitary-gonadal axis, leading to androgen deficiency that may manifest as low libido, impotence, erectile dysfunction, amenorrhea, or infertility. The causal role of opioids in the clinical syndrome of hypogonadism is unknown because the various medical, physical, lifestyle, and psychological stressors that may influence gonadal hormone levels have not been adequately controlled for in studies conducted to date [see Adverse Reactions (6)].

Effects on the Immune System

Opioids have been shown to have a variety of effects on components of the immune system in in vitro and animal models. The clinical significance of these findings is unknown. Overall, the effects of opioids appear to be modestly immunosuppressive.

Concentration–Efficacy Relationships

The minimum effective analgesic concentration will vary widely among patients, especially among patients who have been previously treated with opioid agonists. The minimum effective analgesic concentration of codeine for any individual patient may increase over time due to an increase in pain, the development of a new pain syndrome and/or the development of analgesic tolerance [see Dosage and Administration (2.1, 2.3)].

Concentration–Adverse Reaction Relationships

There is a relationship between increasing codeine plasma concentration and increasing frequency of dose-related opioid adverse reactions such as nausea, vomiting, CNS effects, and respiratory depression. In opioid-tolerant patients, the situation may be altered by the development of tolerance to opioid-related adverse reactions [see Dosage and Administration (2.1, 2.3, 2.5)].

12.3 Pharmacokinetics

The behavior of the individual components is described below.

Butalbital

Absorption

Butalbital is well absorbed from the gastrointestinal tract.

Distribution

Butalbital is expected to distribute to most tissues in the body. Barbiturates in general may appear in breast milk and readily cross the placental barrier. They are bound to plasma and tissue proteins to a varying degree and binding increases directly as a function of lipid solubility.

The in vitro plasma protein binding of butalbital is 45% over the concentration range of 0.5 to 20 mcg/mL. This falls within the range of plasma protein binding (20% to 45%) reported with other barbiturates such as phenobarbital, pentobarbital, and secobarbital sodium. The plasma-to-blood concentration ratio was almost unity indicating that there is no preferential distribution of butalbital into either plasma or blood cells.

Elimination

Elimination of butalbital is primarily via the kidney (59% to 88% of the dose) as unchanged drug or metabolites. The plasma half-life is about 35 hours. Urinary excretion products include parent drug (about 3.6% of the dose), 5-isobutyl-5-(2,3dihydroxypropyl) barbituric acid (about 24% of the dose), 5-allyl-5-(3-hydroxy-2-methyl-1-propyl) barbituric acid (about 4.8% of the dose), products with the barbituric acid ring hydrolyzed with excretion of urea (about 14% of the dose), as well as unidentified materials. Of the material excreted in the urine, 32% is conjugated.

[See Overdosage (10) for toxicity information].

Acetaminophen

Absorption

Acetaminophen is rapidly absorbed from the gastrointestinal tract.

Metabolism

Acetaminophen is primarily metabolized in the liver by first-order kinetics and involves three principal separate pathways: conjugation with glucuronide; conjugation with sulfate; and oxidation via the cytochrome, P450-dependent, mixed-function oxidase enzyme pathway to form a reactive intermediate metabolite, which conjugates with glutathione and is then further metabolized to form cysteine and mercapturic acid conjugates. The principal cytochrome P450 isoenzyme involved appears to be CYP2E1, with CYP1A2 and CYP3A4 as additional pathways.

Distribution

Acetaminophen is distributed throughout most body tissues. A small fraction (10-25%) of acetaminophen is bound to plasma proteins.

Elimination

Elimination of acetaminophen is principally by liver metabolism (conjugation) and subsequent renal excretion of metabolites. Approximately 85% of an oral dose appears in the urine within 24 hours of administration, most as the glucuronide conjugate, with small amounts of other conjugates and unchanged drug. The plasma half-life is 1.25 to 3 hours, but may be increased by liver damage and following overdosage. [See Overdosage (10) for toxicity information].

Caffeine

Absorption

Like most xanthines, caffeine is rapidly absorbed.

Distribution

Caffeine is distributed in all body tissues and fluids, including the CNS, fetal tissues, and breast milk.

Elimination

Caffeine is cleared through metabolism and excretion in the urine.

Metabolism

Caffeine is mainly metabolized by CYP1A2. Other enzymes, including CYP2E1, CYP3A4, CYP2C8 and CYP2C9 may play a minor role in its metabolism. Hepatic biotransformation prior to excretion results in about equal amounts of 1methylxanthine and 1-methyluric acid.

Excretion

Of the 70% of the dose that is recovered in the urine, only 3% is unchanged drug. The plasma half-life is about 3 hours.

[See Overdosage (10) for toxicity information].

Codeine

Absorption

Codeine is readily absorbed from the gastrointestinal tract. At therapeutic doses, the analgesic effect reaches a peak within 2 hours and persists between 4 and 6 hours.

Distribution

Codeine is rapidly distributed from the intravascular spaces to the various body tissues, with preferential uptake by parenchymatous organs such as the liver, spleen and kidney. Codeine crosses the blood-brain barrier, and is found in fetal tissue and breast milk. The plasma concentration does not correlate with brain concentration or relief of pain; however, codeine is not bound to plasma proteins and does not accumulate in body tissues.

Elimination

Metabolism

About 70-80% of administered dose of codeine is metabolized by conjugation with glucuronic acid to codeine-6glucuronide (C6G) and via O-demethylation to morphine (about 5-10%) and N-demethylation to norcodeine (about 10%) respectively. UDP-glucuronosyltransferase (UGT) 2B7 and 2B4 are the major enzymes mediating glucuronidation of codeine to C6G. Cytochrome P450 2D6 is the major enzyme responsible for conversion of codeine to morphine and P450 3A4 is the major enzyme mediating conversion of codeine to norcodeine. Morphine and norcodeine are further metabolized by conjugation with glucuronic acid. The glucuronide metabolites of morphine are morphine-3-glucuronide (M3G) and morphine-6-glucuronide (M6G). Morphine and M6G are known to have analgesic activity in humans. The analgesic activity of C6G in humans is unknown. Norcodeine and M3G are generally not considered to possess analgesic properties.

Excretion

The plasma half-life is about 2.9 hours. The elimination of codeine is primarily via the kidneys, and about 90% of an oral dose is excreted by the kidneys within 24 hours of dosing. The urinary secretion products consist of free and glucuronide conjugated codeine (about 70%), free and conjugated norcodeine (about 10%), free and conjugated morphine (about 10%), normorphine (about 4%), and hydrocodone (1%). The remainder of the dose is excreted in the feces.
[See Overdosage (10) for toxicity information].

13 NONCLINICAL TOXICOLOGY

13.1 Carcinogenesis, Mutagenesis, Impairment of Fertility

Carcinogenesis

Long-term studies in animals to evaluate the carcinogenic potential of the combination of butalbital, acetaminophen, caffeine, and codeine or butalbital alone have not been conducted.

Two-year carcinogenicity studies with codeine sulfate have been conducted in F344/N rats and B6C3F1 mice. There was no evidence of carcinogenicity in male and female rats, respectively, at dietary doses up to 70 and 80 mg/kg/day of codeine sulfate (approximately 4 times the maximum recommended daily dose of 180 mg/day for adults on a mg/m^2 basis) for two years. Similarly there was no evidence of carcinogenicity activity in male and female mice at dietary doses up to 400 mg/kg/day of codeine sulfate (approximately 10 times the maximum recommended daily dose of 180 mg/day for adults on a mg/m^2 basis) for two years.

Long-term studies in mice and rats have been completed by the National Toxicology Program to evaluate the carcinogenic potential of acetaminophen. In 2-year feeding studies, F344/N rats and B6C3F1 mice were fed a diet containing acetaminophen up to 6000 ppm. Female rats demonstrated equivocal evidence of carcinogenic activity based on increased incidences of mononuclear cell leukemia at 1.6 times the maximum human daily dose (MHDD) of 1950 mg/day, based on a body surface area comparison. In contrast, there was no evidence of carcinogenic activity in male rats that received up to 1.4 times or mice at up to 2.4 to 2.8 times the MHDD, based on a body surface area comparison.

In a 2-year study in Sprague-Dawley rats, caffeine (as caffeine base) administered in drinking water was not carcinogenic in male rats at doses up to 102 mg/kg or in female rats at doses up to 170 mg/kg (approximately 4 and 7 times, respectively, the maximum human daily dose on a mg/m^2 basis). In an 18-month study in C57BL/6 mice, no evidence of tumorigenicity was seen at dietary doses up to 55 mg/kg (equivalent to the MHDD on a mg/m^2 basis).

Mutagenesis

There are no genetic toxicology data for butalbital.

Codeine sulfate was not mutagenic in the in vitro bacterial reverse mutation assay or clastogenic in the in vitro Chinese hamster ovary cell chromosome aberration assay.

In the published literature, acetaminophen has been reported to be clastogenic when administered at 1500 mg/kg/day to the rat model (7.2-times the MHDD, based on a body surface area comparison). In contrast, no clastogenicity was noted at a dose of 750 mg/kg/day (3.6-times the MHDD, based on a body surface area comparison), suggesting a threshold effect.

Caffeine (as caffeine base) increased the sister chromatid exchange (SCE) SCE/cell metaphase (exposure time dependent) in an in vivo mouse metaphase analysis. Caffeine also potentiated the genotoxicity of known mutagens and enhanced the micronuclei formation (5-fold) in folate-deficient mice. However, caffeine did not increase chromosomal aberrations in in vitro Chinese hamster ovary cell (CHO) and human lymphocyte assays and was not mutagenic in an in vitro CHO/hypoxanthine guanine phosphoribosyltransferase (HGPRT) gene mutation assay, except at cytotoxic concentrations. In addition, caffeine was not clastogenic in an in vivo mouse micronucleus assay. Caffeine was negative in the in vitro bacterial reverse mutation assay (Ames test).

Impairment of Fertility

No adequate studies have been conducted in animals to characterize the impact of the combinations of butalbital, acetaminophen, caffeine, and codeine on fertility. There are also no data on butalbital alone or codeine alone.

In studies conducted by the National Toxicology Program, fertility assessments with acetaminophen have been completed in Swiss CD-1 mice via a continuous breeding study. There were no effects on fertility parameters in mice consuming up to 3.4 times the MHDD of acetaminophen, based on a body surface area comparison. Although there was no effect on sperm motility or sperm density in the epididymis, there was a significant increase in the percentage of abnormal sperm in mice consuming 3.6 times the MHDD (based on a body surface comparison) and there was a reduction in the number of mating pairs producing a fifth litter at this dose, suggesting the potential for cumulative toxicity with chronic administration of acetaminophen near the upper limit of daily dosing.

Published studies in rodents report that oral acetaminophen treatment of male animals at doses that are 2.4 times the MHDD and greater (based on a body surface comparison) result in decreased testicular weights, reduced spermatogenesis, reduced fertility, and reduced implantation sites in females given the same doses. These effects appear to increase with the duration of treatment. The clinical significance of these findings is not known.

Caffeine (as caffeine base) administered to male rats at 50 mg/kg/day subcutaneously (2 times the MHDD on a mg/m^2 basis) for 4 days prior to mating with untreated females, caused decreased male reproductive performance in addition to causing embryotoxicity. In addition, long-term exposure to high oral doses of caffeine (3 g over 7 weeks) was toxic to rat testes as manifested by spermatogenic cell degeneration.

16 HOW SUPPLIED/STORAGE AND HANDLING

Butalbital, Acetaminophen, Caffeine, and Codeine Phosphate Capsules:
Dark blue, opaque cap is imprinted with “WATSON” in light blue. White, opaque body is imprinted with “3220” in red. Bottles of 100 are supplied with child-resistant closures (NDC 0591-3220-01).

Store below 30°C (86°F); and dispense in a tight container.

Store Butalbital, Acetaminophen, Caffeine, and Codeine Phosphate Capsules securely and dispose of properly.

17 PATIENT COUNSELING INFORMATION

Advise the patient to read the FDA-approved patient labeling (Medication Guide).

Storage and Disposal

Because of the risks associated with accidental ingestion, misuse, and abuse, advise patients to store Butalbital, Acetaminophen, Caffeine, and Codeine Phosphate Capsules securely, out of sight and reach of children, and in a location not accessible by others, including visitors to the home [see Warnings and Precautions (5.1, 5.2), Drug Abuse and Dependence (9.2)]. Inform patients that leaving Butalbital, Acetaminophen, Caffeine, and Codeine Phosphate Capsules unsecured can pose a deadly risk to others in the home.

Advise patients and caregivers that when medicines are no longer needed, they should be disposed of promptly. Inform patients that medicine take-back options are the preferred way to safely dispose of most types of unneeded medicines. If no take back programs or DEA-registered collectors are available, instruct patients to dispose of Butalbital, Acetaminophen, Caffeine, and Codeine Phosphate Capsules by following these four steps:

- Mix Butalbital, Acetaminophen, Caffeine, and Codeine Phosphate Capsules (do not crush) with an unpalatable substance such as dirt, cat litter, or used coffee grounds;
- Place the mixture in a container such as a sealed plastic bag;
- Throw the container in the household trash;
- Remove all personal information on the prescription label of the empty bottle

Inform patients that they can visit www.fda.gov/drugdisposal for additional information on disposal of unused medicines.

Addiction, Abuse, and Misuse

Inform patients that the use of Butalbital, Acetaminophen, Caffeine, and Codeine Phosphate Capsules, even when taken as recommended, can result in addiction, abuse, and misuse, which can lead to overdose and death [see Warnings and Precautions (5.1)]. Instruct patients not to share Butalbital, Acetaminophen, Caffeine, and Codeine Phosphate Capsules with others and to take steps to protect Butalbital, Acetaminophen, Caffeine, and Codeine Phosphate Capsules from theft or misuse.

Life-Threatening Respiratory Depression

Inform patients of the risk of life-threatening respiratory depression, including information that the risk is greatest when starting Butalbital, Acetaminophen, Caffeine, and Codeine Phosphate Capsules or when the dosage is increased, and that it can occur even at recommended dosages.

Educate patients and caregivers on how to recognize respiratory depression and emphasize the importance of calling 911 or getting emergency medical help right away in the event of a known or suspected overdose [see Warnings and Precautions (5.2)].

Accidental Ingestion

Inform patients that accidental ingestion, especially by children, may result in respiratory depression or death [see Warnings and Precautions (5.2)].

Risks from Concomitant Use with Benzodiazepines or Other CNS Depressants

Inform patients and caregivers that potentially fatal additive effects may occur if Butalbital, Acetaminophen, Caffeine, and Codeine Phosphate Capsules are used with benzodiazepines or other CNS depressants, including alcohol (e.g., non-benzodiazepine sedative/hypnotics, anxiolytics, tranquilizers, muscle relaxants, general anesthetics, antipsychotics, gabapentinoids [gabapentin or pregabalin], and other opioids), and not to use these concomitantly unless supervised by a healthcare provider [see Warnings and Precautions (5.3), Drug Interactions (7)].

Patient Access to an Opioid Overdose Reversal Agent for the Emergency Treatment of Opioid Overdose

Inform patients and caregivers about opioid overdose reversal agents (e.g., naloxone, nalmefene). Discuss the importance of having access to an opioid overdose reversal agent, especially if the patient has risk factors for overdose (e.g., concomitant use of CNS depressants, a history of opioid use disorder, or prior opioid overdose) or if there are household members (including children) or other close contacts at risk for accidental ingestion or opioid overdose.

Discuss with the patient the options for obtaining an opioid overdose reversal agent (e.g., prescription, over-the-counter, or as part of a community-based program) [see Dosage and Administration (2.2), Warnings and Precautions (5.3)].

Educate patients and caregivers on how to recognize the signs and symptoms of an overdose.

Explain to patients and caregivers that the effects of opioid overdose reversal agents like naloxone and nalmefene are temporary, and that they must call 911 or get emergency medical help right away in all cases of known or suspected opioid overdose, even if an opioid overdose reversal agent is administered [see Overdosage (10)].

Advise patients and caregivers:

- how to treat with their overdose reversal agent in the event of an opioid overdose
- to tell family and friends about their opioid overdose reversal agent, and to keep it in a place where family and friends can access it in an emergency
- to read the Patient Information (or other educational material) that will come with their opioid overdose reversal agent. Emphasize the importance of doing this before an opioid emergency happens, so the patient and caregiver will know what to do.

Ultra-Rapid Metabolism of Codeine and Other Risk Factors for Life-threatening Respiratory Depression in Children

Advise caregivers that Butalbital, Acetaminophen, Caffeine, and Codeine Phosphate Capsules are contraindicated in all children younger than 12 years of age and in children younger than 18 years of age following tonsillectomy and/or adenoidectomy. Advise caregivers of children 12-18 years of age receiving codeine to watch for signs of respiratory depression [see Warnings and Precautions (5.6)].

Hyperalgesia and Allodynia

Inform patients and caregivers not to increase opioid dosage without first consulting a clinician. Advise patients to seek medical attention if they experience symptoms of hyperalgesia, including worsening pain, increased sensitivity to pain, or new pain [see Warnings and Precautions (5.9), Adverse Reactions (6)].

Serotonin Syndrome

Inform patients that opioids could cause a rare but potentially life-threatening condition called serotonin syndrome resulting from concomitant administration of serotonergic drugs. Warn patients of the symptoms of serotonin syndrome and to seek medical attention right away if symptoms develop. Instruct patients to inform their healthcare providers if they are taking, or plan to take serotonergic medications [see Drug Interactions (7)].

MAOI Interaction

Inform patients not to take Butalbital, Acetaminophen, Caffeine, and Codeine Phosphate Capsules while using any drugs that inhibit monoamine oxidase. Patients should not start MAOIs while taking Butalbital, Acetaminophen, Caffeine, and Codeine Phosphate Capsules [see Drug Interactions (7)].

Important Administration Instructions

Instruct patients how to properly take Butalbital, Acetaminophen, Caffeine, and Codeine Phosphate Capsules, including the following:

- To take the drug only for as long as it is prescribed, in the amounts prescribed, and no more frequently than prescribed [see Dosage and Administration (2.1, 2.3)].
- Do not take more than 4000 milligrams of acetaminophen per day and to call their healthcare provider if they took more than the recommended dose.

Important Discontinuation Instructions

In order to avoid developing withdrawal symptoms, instruct patients not to discontinue Butalbital, Acetaminophen, Caffeine, and Codeine Phosphate Capsules without first discussing a tapering plan with the prescriber [see Dosage and Administration (2.5)].

Risks of Driving and Operating Heavy Machinery

Inform patients that Butalbital, Acetaminophen, Caffeine, and Codeine Phosphate Capsules may impair the ability to perform potentially hazardous activities such as driving a car or operating heavy machinery. Advise patients not to perform such tasks until they know how they will react to the medication [see Warnings and Precautions (5.19)].

Constipation

Advise patients of the potential for severe constipation, including management instructions and when to seek medical attention [see Adverse Reactions (6)].

Adrenal Insufficiency

Inform patients that opioids could cause adrenal insufficiency, a potentially life-threatening condition. Adrenal insufficiency may present with non-specific symptoms and signs such as nausea, vomiting, anorexia, fatigue, weakness, dizziness, and low blood pressure. Advise patients to seek medical attention if they experience a constellation of these symptoms [see Warnings and Precautions (5.12)].

Severe Hypotension

Inform patients that Butalbital, Acetaminophen, Caffeine, and Codeine Phosphate Capsules may cause orthostatic hypotension and syncope. Instruct patients how to recognize symptoms of low blood pressure and how to reduce the risk of serious consequences should hypotension occur (e.g., sit or lie down, carefully rise from a sitting or lying position) [see Warnings and Precautions (5.13)].

Anaphylaxis

Inform patients that anaphylaxis has been reported with ingredients contained in Butalbital, Acetaminophen, Caffeine, and Codeine Phosphate Capsules. Advise patients how to recognize such a reaction and when to seek medical attention [see Contraindications (4), Adverse Reactions (6)].

Pregnancy

Neonatal Opioid Withdrawal Syndrome

Inform female patients of reproductive potential that use of Butalbital, Acetaminophen, Caffeine, and Codeine Phosphate Capsules for an extended period of time during pregnancy can result in neonatal opioid withdrawal syndrome, which may be life-threatening if not recognized and treated [see Warnings and Precautions (5.4), Use in Specific Populations (8.1)].

Embryo-Fetal Toxicity

Inform female patients of reproductive potential that Butalbital, Acetaminophen, Caffeine, and Codeine Phosphate Capsules can cause fetal harm and to inform their healthcare provider of a known or suspected pregnancy [see Use in Specific Populations (8.1)].

Lactation

Advise women that breastfeeding is not recommended during treatment with Butalbital, Acetaminophen, Caffeine, and Codeine Phosphate Capsules [see Use in Specific Populations (8.2)].

Infertility

Inform patients that use of opioids for an extended period of time may cause reduced fertility. It is not known whether these effects on fertility are reversible [see Adverse Reactions (6)].

Dispense with Medication Guide available at: www.tevausa.com/medguides

Distributed By: Actavis Pharma LLC
Parsippany, NJ 07054

©2026 Teva Pharmaceuticals USA, Inc.

Medication Guide

Dispense with Medication Guide available at: www.tevausa.com/medguides

Medication Guide

Butalbital, Acetaminophen, Caffeine, and Codeine Phosphate Capsules, C III

Butalbital, Acetaminophen, Caffeine, and Codeine Phosphate Capsules are:

- A strong prescription pain medicine that contains an opioid (narcotic) that is indicated for the relief of the symptom complex of tension (or muscle contraction) headache, when other pain treatments such as non-opioid pain medicines do not treat your pain well enough or you cannot tolerate them.
- An opioid pain medicine that can put you at risk for overdose and death. Even if you take your dose correctly as prescribed you are at risk for opioid addiction, abuse, and misuse that can lead to death.

Important information about Butalbital, Acetaminophen, Caffeine, and Codeine Phosphate Capsules:

- Get emergency help or call 911 right away if you take too much Butalbital, Acetaminophen, Caffeine, and Codeine Phosphate Capsules (overdose). When you first start taking Butalbital, Acetaminophen, Caffeine, and Codeine Phosphate Capsules, when your dose is changed, or if you take too much (overdose), serious or life-threatening breathing problems that can lead to death may occur. Ask your healthcare provider about medicines like naloxone or nalmefene that can be used in an emergency to reverse an opioid overdose.
- Taking Butalbital, Acetaminophen, Caffeine, and Codeine Phosphate Capsules with other opioid medicines, benzodiazepines, gabapentinoids (gabapentin or pregabalin), alcohol, or other central nervous system depressants (including street drugs) can cause severe drowsiness, decreased awareness, breathing problems, coma, and death.
- Never give anyone else your Butalbital, Acetaminophen, Caffeine, and Codeine Phosphate Capsules. They could die from taking it. Selling or giving away Butalbital, Acetaminophen, Caffeine, and Codeine Phosphate Capsules is against the law.
- Store Butalbital, Acetaminophen, Caffeine, and Codeine Phosphate Capsules securely, out of sight and reach of children, and in a location not accessible by others, including visitors to the home.
- Get emergency help right away if you take more than 4,000 mg of acetaminophen in 1 day. Taking Butalbital, Acetaminophen, Caffeine, and Codeine Phosphate Capsules with other products that contain acetaminophen can lead to serious liver problems and death.

Important Information Guiding Use in Pediatric Patients:

- Do not give Butalbital, Acetaminophen, Caffeine, and Codeine Phosphate Capsules to a child younger than 12 years of age.
- Do not give Butalbital, Acetaminophen, Caffeine, and Codeine Phosphate Capsules to a child younger than 18 years of age after surgery to remove the tonsils and/or adenoids.
- Avoid giving Butalbital, Acetaminophen, Caffeine, and Codeine Phosphate Capsules to children between 12 to 18 years of age who have risk factors for breathing problems such as obstructive sleep apnea, obesity, or underlying lung problems.

Do not take Butalbital, Acetaminophen, Caffeine, and Codeine Phosphate Capsules if you have:

- severe asthma, trouble breathing, or other lung problems.
- a bowel blockage or have narrowing of the stomach or intestines.

Before taking Butalbital, Acetaminophen, Caffeine, and Codeine Phosphate Capsules, tell your healthcare provider if you have a history of:

- head injury, seizures
- problems urinating
- abuse of street or prescription drugs, alcohol addiction, opioid overdose, or mental health problems.
- Have been told by your healthcare provider that you are a “rapid metabolizer” of certain medicines
- liver, kidney, thyroid problems
- pancreas or gallbladder problems

Tell your healthcare provider if you are:

- Noticing your pain getting worse. If your pain gets worse after you take Butalbital, Acetaminophen, Caffeine, and Codeine Phosphate Capsules, do not take more of Butalbital, Acetaminophen, Caffeine, and Codeine Phosphate Capsules without first talking to your healthcare provider. Talk to your healthcare provider if the pain that you have increases, if you feel more sensitive to pain, or if you have new pain after taking Butalbital, Acetaminophen, Caffeine, and Codeine Phosphate Capsules.
- pregnant or planning to become pregnant. Use of Butalbital, Acetaminophen, Caffeine, and Codeine Phosphate Capsules for an extended period of time during pregnancy can cause withdrawal symptoms in your newborn baby that could be life-threatening if not recognized and treated.
- breastfeeding. Not recommended during treatment with Butalbital, Acetaminophen, Caffeine, and Codeine Phosphate Capsules; may harm your baby.
- living in a household where there are small children or someone who has abused street or prescription drugs.
- taking prescription or over-the-counter medicines, vitamins, or herbal supplements. Taking Butalbital, Acetaminophen, Caffeine, and Codeine Phosphate Capsules with certain other medicines can cause serious side effects that could lead to death.

When taking Butalbital, Acetaminophen, Caffeine, and Codeine Phosphate Capsules:

- Do not change your dose. Take Butalbital, Acetaminophen, Caffeine, and Codeine Phosphate Capsules exactly as prescribed by your healthcare provider. Use the lowest dose possible for the shortest time needed.
- For acute (short-term) pain, you may only need to take Butalbital, Acetaminophen, Caffeine, and Codeine Phosphate Capsules for a few days. You may have some Butalbital, Acetaminophen, Caffeine, and Codeine Phosphate Capsules left over that you did not use. See disposal information at the bottom of this section for directions on how to safely throw away (dispose of) your unused Butalbital, Acetaminophen, Caffeine, and Codeine Phosphate Capsules.
- Take your prescribed dose of 1 or 2 capsules every 4 hours. Total daily dosage should not exceed 6 capsules. Do not take more than your prescribed dose. If you miss a dose, take your next dose at your usual time.
- Call your healthcare provider if the dose you are taking does not control your pain.
- If you have been taking Butalbital, Acetaminophen, Caffeine, and Codeine Phosphate Capsules regularly, do not stop taking Butalbital, Acetaminophen, Caffeine, and Codeine Phosphate Capsules without talking to your healthcare provider.
- After you stop taking Butalbital, Acetaminophen, Caffeine, and Codeine Phosphate Capsules, dispose the unused Butalbital, Acetaminophen, Caffeine, and Codeine Phosphate Capsules in accordance with the local state guidelines and/or regulations.
- Dispose of expired, unwanted, or unused Butalbital, Acetaminophen, Caffeine, and Codeine Phosphate Capsules by taking your drug to an authorized DEA-registered collector or drug take-back program. If one is not available, you can dispose of Butalbital, Acetaminophen, Caffeine, and Codeine Phosphate Capsules by mixing the product with dirt, cat litter, or coffee grounds; placing the mixture in a sealed plastic bag, and throwing the bag in your trash. Visit www.fda.gov/drugdisposal for additional information on disposal of unused medicines.

While taking Butalbital, Acetaminophen, Caffeine, and Codeine Phosphate Capsules DO NOT:

- Drive or operate heavy machinery, until you know how Butalbital, Acetaminophen, Caffeine, and Codeine Phosphate Capsules affect you. Butalbital, Acetaminophen, Caffeine, and Codeine Phosphate Capsules can make you sleepy, dizzy, or lightheaded.
- Drink alcohol or use prescription or over-the-counter medicines that contain alcohol. Using products containing alcohol during treatment with Butalbital, Acetaminophen, Caffeine, and Codeine Phosphate Capsules may cause you to overdose and die.

The possible side effects of Butalbital, Acetaminophen, Caffeine, and Codeine Phosphate Capsules:

- constipation, nausea, sleepiness, vomiting, tiredness, headache, dizziness, abdominal pain. Call your healthcare provider if you have any of these symptoms and they are severe.

Get emergency medical help or call 911 right away if you:

- have trouble breathing, shortness of breath, fast heartbeat, chest pain, swelling of your face, tongue, or throat, extreme drowsiness, light-headedness when changing positions, feeling faint, agitation, high body temperature, trouble walking, stiff muscles, or mental changes such as confusion.
- are a nursing mother taking Butalbital, Acetaminophen, Caffeine, and Codeine Phosphate Capsules, and your breastfeeding baby has increased sleepiness, confusion, difficulty breathing, shallow breathing, limpness, or difficulty breastfeeding.

These are not all the possible side effects of Butalbital, Acetaminophen, Caffeine, and Codeine Phosphate Capsules. Call your doctor for medical advice about side effects. You may report side effects to FDA at 1-800-FDA-1088. For more information go to dailymed.nlm.nih.gov

Distributed by: Actavis Pharma LLC, Parsippany, NJ 07054

©2026 Teva Pharmaceuticals USA, Inc.

This Medication Guide has been approved by the U.S. Food and Drug Administration.

Revised: 1/2026

Package/Label Display Panel

NDC 0591-3220-01
CIII
50mg, 325mg, 40mg, 30mg
Butalbital, Acetaminophen, Caffeine, and Codeine Phosphate Capsules
Medication Guide Required: Dispense the accompanying Medication Guide to each patient.
Actavis
100 Capsules
Rx Only